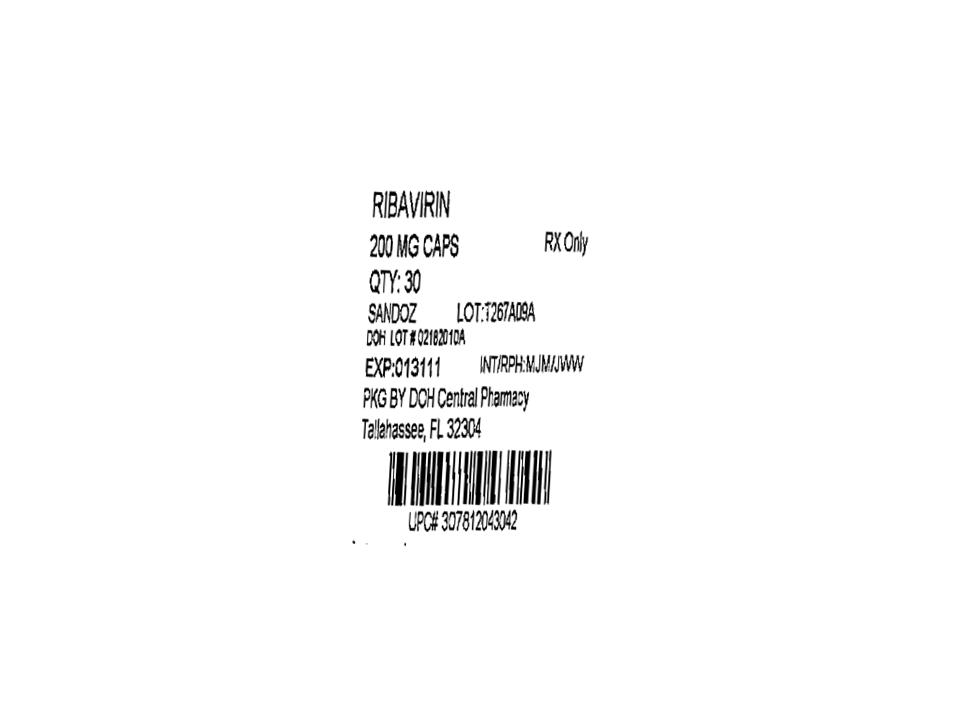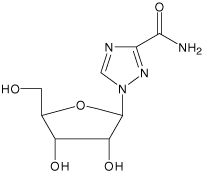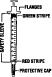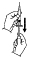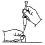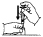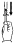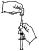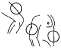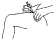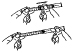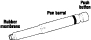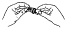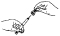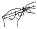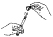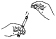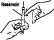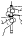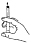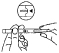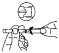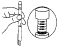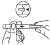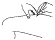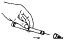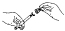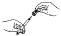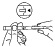 DRUG LABEL: Ribavirin
NDC: 53808-0781 | Form: CAPSULE
Manufacturer: State of Florida DOH Central Pharmacy
Category: prescription | Type: HUMAN PRESCRIPTION DRUG LABEL
Date: 20100608

ACTIVE INGREDIENTS: RIBAVIRIN 200 mg/1 1
INACTIVE INGREDIENTS: CROSCARMELLOSE SODIUM; FD&C BLUE NO. 1; GELATIN; HYPROMELLOSE; MAGNESIUM STEARATE; MANNITOL; POVIDONE; PROPYLENE GLYCOL; SHELLAC; TITANIUM DIOXIDE

Ribavirin Capsules
200 mg

BOXED WARNING

- Ribavirin monotherapy is not effective for the treatment of chronic hepatitis C virus infection and should not be used alone for this indication. (See WARNINGS).
- The primary toxicity of ribavirin is hemolytic anemia. The anemia associated with ribavirin therapy may result in worsening of cardiac disease that has lead to fatal and nonfatal myocardial infarctions. Patients with a history of significant or unstable cardiac disease should not be treated with ribavirin. (See WARNINGS, ADVERSE REACTIONS, and DOSAGE AND ADMINISTRATION).
- Significant teratogenic and/or embryocidal effects have been demonstrated in all animal species exposed to ribavirin. In addition, ribavirin has a multiple-dose half-life of 12 days, and so it may persist in nonplasma compartments for as long as 6 months. Therefore, ribavirin therapy is contraindicated in women who are pregnant and in the male partners of women who are pregnant. Extreme care must be taken to avoid pregnancy during therapy and for 6 months after completion of treatment in both female patients and in female partners of male patients who are taking ribavirin therapy. At least two reliable forms of effective contraception must be utilized during treatment and during the 6-month posttreatment follow-up period. (See CONTRAINDICATIONS, WARNINGS, PRECAUTIONS: Information for Patients and Pregnancy Category X).

DESCRIPTION

Ribavirin is a nucleoside analog. The chemical name of ribavirin is 1-β-D-ribofuranosyl-1H-1,2,4-triazole-3-carboxamide and has the following structural formula:

Ribavirin is a white, crystalline powder. It is freely soluble in water and slightly soluble in anhydrous alcohol. The empirical formula is C8H12N4O5 and the molecular weight is 244.21.

Ribavirin capsules consist of white powder in a white, opaque, gelatin capsule. Each capsule, for oral administration, contains 200 mg ribavirin. In addition, each capsule contains the following inactive ingredients: croscarmellose sodium, hypromellose, magnesium stearate, mannitol and povidone. The capsule shell consists of gelatin and titanium dioxide. The capsule is printed with edible blue pharmaceutical ink which is made of FD&C Blue #2 aluminum lake, propylene glycol, shellac and titanium dioxide.

Mechanism of Action

The mechanism of inhibition of hepatitis C virus (HCV) RNA by combination therapy with ribavirin and interferon products has not been established.

CLINICAL PHARMACOLOGY

Ribavirin

Single- and multiple-dose pharmacokinetic properties in adults are summarized in TABLE 1. Ribavirin was rapidly and extensively absorbed following oral administration. However, due to first-pass metabolism, the absolute bioavailability averaged 64% (44%) [In this section of the label, numbers in parenthesis indicate % coefficient of variation.] . There was a linear relationship between dose and AUCtf (AUC from time zero to last measurable concentration) following single doses of 200 to 1200 mg ribavirin. The relationship between dose and Cmax was curvilinear, tending to asymptote above single doses of 400 to 600 mg.

Upon multiple oral dosing, based on AUC12hr, a sixfold accumulation of ribavirin was observed in plasma. Following oral dosing with 600 mg BID, steady-state was reached by approximately 4 weeks, with mean steady-state plasma concentrations of 2200 (37%) ng/mL. Upon discontinuation of dosing, the mean half-life was 298 (30%) hours, which probably reflects slow elimination from nonplasma compartments.

Effect of Food on Absorption of Ribavirin

Both AUCtf and Cmax increased by 70% when ribavirin capsules were administered with a high-fat meal (841 kcal, 53.8 g fat, 31.6 g protein, and 57.4 g carbohydrate) in a single-dose pharmacokinetic study. There are insufficient data to address the clinical relevance of these results. Clinical efficacy studies with ribavirin/INTRON® A (interferon alfa-2b, recombinant) were conducted without instructions with respect to food consumption. During clinical studies with ribavirin/INTRON A, all subjects were instructed to take ribavirin capsules with food. (See DOSAGE AND ADMINISTRATION).

Effect of Antacid on Absorption of Ribavirin

Coadministration of ribavirin capsules with an antacid containing magnesium, aluminum, and simethicone (Mylanta®) resulted in a 14% decrease in mean ribavirin AUCtf. The clinical relevance of results from this single-dose study is unknown.

TABLE 1. Mean (% CV) Pharmacokinetic Parameters for Ribavirin Capsules when Administered Individually to Adults
 | Ribavirin Capsules
Parameter | Single Dose; 600 mg; Capsules; (N=12) | Multiple Dose; 600 mg BID; Capsules; (N=12)
Tmax (hr) | 1.7 (46) [N=11] | 3 (60)
Cmax [ng/mL] | 782 (37) | 3680 (85)
AUCtf [ng•hr/mL] | 13400 (48) | 228000 (25)
T1/2 (hr) | 43.6 (47) | 298 (30)
Apparent Volume of Distribution (L) | 2825 (9) [data obtained from a single-dose pharmacokinetic study using ^14C labeled ribavirin; N=5]
Apparent Clearance (L/hr) | 38.2 (40)
Absolute Bioavailability | 64% (44) [N=6]

Ribavirin transport into nonplasma compartments has been most extensively studied in red blood cells, and has been identified to be primarily via an es-type equilibrative nucleoside transporter. This type of transporter is present on virtually all cell types and may account for the extensive volume of distribution. Ribavirin does not bind to plasma proteins.

Ribavirin has two pathways of metabolism: (i) a reversible phosphorylation pathway in nucleated cells; and (ii) a degradative pathway involving deribosylation and amide hydrolysis to yield a triazole carboxylic acid metabolite. Ribavirin and its triazole carboxamide and triazole carboxylic acid metabolites are excreted renally. After oral administration of 600 mg of ^14C-ribavirin, approximately 61% and 12% of the radioactivity was eliminated in the urine and feces, respectively, in 336 hours. Unchanged ribavirin accounted for 17% of the administered dose.

Results of in vitro studies using both human and rat liver microsome preparations indicated little or no cytochrome P450 enzyme-mediated metabolism of ribavirin, with minimal potential for P450 enzyme-based drug interactions.

No pharmacokinetic interactions were noted between INTRON A injection and ribavirin capsules in a multiple-dose pharmacokinetic study.

Drug Interactions

Ribavirin has been shown in vitro to inhibit phosphorylation of zidovudine and stavudine which could lead to decreased antiretroviral activity. Exposure to didanosine or its active metabolite (dideoxyadenosine 5’-triphosphate) is increased when didanosine is coadministered with ribavirin, which could cause or worsen clinical toxicities (see PRECAUTIONS: Drug Interactions).

Renal Dysfunction

The pharmacokinetics of ribavirin were assessed after administration of a single oral dose (400 mg) of ribavirin to non HCV-infected subjects with varying degrees of renal dysfunction. The mean AUCtf value was threefold greater in subjects with creatinine clearance values between 10 to 30 mL/min when compared to control subjects (creatinine clearance >90 mL/min). In subjects with creatinine clearance values between 30 to 60 mL/min, AUCtf was twofold greater when compared to control subjects. The increased AUCtf appears to be due to reduction of renal and non-renal clearance in these patients. Phase III efficacy trials included subjects with creatinine clearance values >50 mL/min. The multiple dose pharmacokinetics of ribavirin cannot be accurately predicted in patients with renal dysfunction. Ribavirin is not effectively removed by hemodialysis. Patients with creatinine clearance <50 mL/min should not be treated with ribavirin (See WARNINGS).

Hepatic Dysfunction

The effect of hepatic dysfunction was assessed after a single oral dose of ribavirin (600 mg). The mean AUCtf values were not significantly different in subjects with mild, moderate, or severe hepatic dysfunction (Child-Pugh Classification A, B, or C) when compared to control subjects. However, the mean Cmax values increased with severity of hepatic dysfunction and was twofold greater in subjects with severe hepatic dysfunction when compared to control subjects.

Elderly Patients

Pharmacokinetic evaluations in elderly subjects have not been performed.

Gender

There were no clinically significant pharmacokinetic differences noted in a single-dose study of eighteen male and eighteen female subjects.

INDICATIONS AND USAGE

Ribavirin capsules are indicated in combination with INTRON A (interferon alfa-2b, recombinant) Injection for the treatment of chronic hepatitis C in patients 18 years of age and older with compensated liver disease previously untreated with alpha interferon or in patients 18 years of age and older who have relapsed following alpha interferon therapy.

The safety and efficacy of ribavirin capsules with non-pegylated interferons other than the INTRON A product have not been established.

Previously Untreated Patients

Adults with compensated chronic hepatitis C and detectable HCV RNA (assessed by a central laboratory using a research-based RT-PCR assay) who were previously untreated with alpha interferon therapy were enrolled into two multi-center, double-blind trials (US and International) and randomized to receive ribavirin capsules 1200 mg/day (1000 mg/day for patients weighing ≤75 kg) plus INTRON A Injection 3 MIU TIW or INTRON A Injection plus placebo for 24 or 48 weeks followed by 24 weeks of off-therapy follow-up. The International study did not contain a 24-week INTRON A plus placebo treatment arm. The US study enrolled 912 patients who, at baseline, were 67% male, 89% Caucasian with a mean Knodell HAI score (I+II+III) of 7.5, and 72% genotype 1. The International study, conducted in Europe, Israel, Canada, and Australia, enrolled 799 patients (65% male, 95% Caucasian, mean Knodell score 6.8, and 58% genotype 1).

Study results are summarized in TABLE 2.

TABLE 2. Virologic and Histologic Responses: Previously Untreated Patients [Number (%) of patients.]
 | US Study |  |  |  | International Study
 | 24 weeks of treatment |  | 48 weeks of treatment |  | 24 weeks of; treatment | 48 weeks of treatment
 | INTRON A; plus; Ribavirin; (N=228) | INTRON A; plus; Placebo; (N=231) | INTRON A; plus; Ribavirin; (N=228) | INTRON A; plus; Placebo; (N=225) | INTRON A; plus; Ribavirin; (N=265) | INTRON A; plus; Ribavirin; (N=268) | INTRON A; plus; Placebo; (N=266)
Virologic; Response
Responder [Defined as HCV RNA below limit of detection using a research based RT-PCR assay at end of treatment and during follow-up period.] | 65 (29) | 13 (6) | 85 (37) | 27 (12) | 86 (32) | 113 (42) | 46 (17)
Nonresponder | 147 (64) | 194 (84) | 110 (48) | 168 (75) | 158 (60) | 120 (45) | 196 (74)
Missing Data | 16 (7) | 24 (10) | 33 (14) | 30 (13) | 21 (8) | 35 (13) | 24 (9)
Histologic; Response
Improvement [Defined as posttreatment (end of follow-up) minus pretreatment liver biopsy Knodell HAI score (I+II+III) improvement of ≥2 points.] | 102 (45) | 77 (33) | 96 (42) | 65 (29) | 103 (39) | 102 (38) | 69 (26)
No improvement | 77 (34) | 99 (43) | 61 (27) | 93 (41) | 85 (32) | 58 (22) | 111 (41)
Missing Data | 49 (21) | 55 (24) | 71 (31) | 67 (30) | 77 (29) | 108 (40) | 86 (32)

Of patients who had not achieved HCV RNA below the limit of detection of the research based assay by week 24 of ribavirin/INTRON A treatment, less than 5% responded to an additional 24 weeks of combination treatment.

Among patients with HCV Genotype 1 treated with ribavirin/INTRON A therapy who achieved HCV RNA below the detection limit of the research-based assay by 24 weeks, those randomized to 48 weeks of treatment had higher virologic responses compared to those in the 24 week treatment group. There was no observed increase in response rates for patients with HCV nongenotype 1 randomized to ribavirin/INTRON A therapy for 48 weeks compared to 24 weeks.

Relapse Patients

Patients with compensated chronic hepatitis C and detectable HCV RNA (assessed by a central laboratory using a research-based RT-PCR assay) who had relapsed following one or two courses of interferon therapy (defined as abnormal serum ALT levels) were enrolled into two multicenter, double-blind trials (US and International) and randomized to receive ribavirin 1200 mg/day (1000 mg/day for patients weighing ≤75 kg) plus INTRON A 3 MIU TIW or INTRON A plus placebo for 24 weeks followed by 24 weeks of off-therapy follow-up. The US study enrolled 153 patients who, at baseline, were 67% male, 92% Caucasian with a mean Knodell HAI score (I+II+III) of 6.8, and 58% genotype 1. The International study, conducted in Europe, Israel, Canada, and Australia, enrolled 192 patients (64% male, 95% Caucasian, mean Knodell score 6.6, and 56% genotype 1).

Study results are summarized in TABLE 3.

TABLE 3. Virologic and Histologic Responses: Relapse Patients [Number (%) of patients.]
 | US Study |  | International Study
 | INTRON A; plus; Ribavirin; (N=77) | INTRON A; plus; Placebo; (N=76) | INTRON A; plus; Ribavirin; (N=96) | INTRON A; plus; Placebo; (N=96)
Virologic; Response
Responder [Defined as HCV RNA below limit of detection using a research based RT-PCR assay at end of treatment and during follow-up period.] | 33 (43) | 3 (4) | 46 (48) | 5 (5)
Nonresponder | 36 (47) | 66 (87) | 45 (47) | 91 (95)
Missing Data | 8 (10) | 7 (9) | 5 (5) | 0 (0)
Histologic; Response
Improvement [Defined as posttreatment (end of follow-up) minus pretreatment liver biopsy Knodell HAI score (I+II+III) improvement of ≥2 points.] | 38 (49) | 27 (36) | 49 (51) | 30 (31)
No improvement | 23 (30) | 37 (49) | 29 (30) | 44 (46)
Missing Data | 16 (21) | 12 (16) | 18 (19) | 22 (23)

Virologic and histologic responses were similar among male and female patients in both the previously untreated and relapse studies.

CONTRAINDICATIONS

Pregnancy

Ribavirin capsules may cause birth defects and/or death of the exposed fetus. Ribavirin therapy is contraindicated for use in women who are pregnant or in men whose female partners are pregnant. (See WARNINGS, PRECAUTIONS: Information for Patients and Pregnancy Category X).

Ribavirin capsules are contraindicated in patients with a history of hypersensitivity to ribavirin or any component of the capsule.

Patients with autoimmune hepatitis must not be treated with combination ribavirin/INTRON A therapy because using these medicines can make the hepatitis worse.

Patients with hemoglobinopathies (e.g., thalassemia major, sickle-cell anemia) should not be treated with ribavirin capsules.

WARNINGS

Based on results of clinical trials ribavirin monotherapy is not effective for the treatment of chronic hepatitis C virus infection; therefore, ribavirin capsules must not be used alone. The safety and efficacy of ribavirin capsules with non-pegylated interferons other than INTRON A product have not been established.

There are significant adverse events caused by ribavirin/INTRON A therapy, including severe depression and suicidal ideation, hemolytic anemia, suppression of bone marrow function, autoimmune and infectious disorders, pulmonary dysfunction, pancreatitis, and diabetes. Suicidal ideation or attempts occurred more frequently among pediatric patients, primarily adolescents, compared to adult patients (2.4% versus 1%) during treatment and off-therapy follow-up. The Appendix to this package insert should be reviewed in its entirety prior to initiation of therapy of ribavirin capsules taken together with INTRON A for additional safety information.

Pregnancy

Ribavirin capsules may cause birth defects and/or death of the exposed fetus. Extreme care must be taken to avoid pregnancy in female patients and in female partners of male patients. Ribavirin capsules have demonstrated significant teratogenic and/or embryocidal effects in all animal species in which adequate studies have been conducted. These effects occurred at doses as low as one twentieth of the recommended human dose of ribavirin. RIBAVIRIN THERAPY SHOULD NOT BE STARTED UNTIL A REPORT OF A NEGATIVE PREGNANCY TEST HAS BEEN OBTAINED IMMEDIATELY PRIOR TO PLANNED INITIATION OF THERAPY. Patients should be instructed to use at least two forms of effective contraception during treatment and during the six month period after treatment has been stopped based on multiple dose half-life of ribavirin of 12 days. Pregnancy testing should occur monthly during ribavirin therapy and for six months after therapy has stopped (see CONTRAINDICATIONS and PRECAUTIONS: Information for Patients and Pregnancy Category X).

Anemia

The primary toxicity of ribavirin is hemolytic anemia, which was observed in approximately 10% of ribavirin/INTRON A-treated patients in clinical trials (see ADVERSE REACTIONS: Laboratory Values: Hemoglobin). The anemia associated with ribavirin capsules occurs within 1 to 2 weeks of initiation of therapy. BECAUSE THE INITIAL DROP IN HEMOGLOBIN MAY BE SIGNIFICANT, IT IS ADVISED THAT HEMOGLOBIN OR HEMATOCRIT BE OBTAINED PRETREATMENT AND AT WEEK 2 AND WEEK 4 OF THERAPY, OR MORE FREQUENTLY IF CLINICALLY INDICATED. Patients should then be followed as clinically appropriate.

Fatal and nonfatal myocardial infarctions have been reported in patients with anemia caused by ribavirin. Patients should be assessed for underlying cardiac disease before initiation of ribavirin therapy. Patients with pre-existing cardiac disease should have electrocardiograms administered before treatment, and should be appropriately monitored during therapy. If there is any deterioration of cardiovascular status, therapy should be suspended or discontinued. (See DOSAGE AND ADMINISTRATION: Guidelines for Dose Modification). Because cardiac disease may be worsened by drug induced anemia, patients with a history of significant or unstable cardiac disease should not use ribavirin. (See ADVERSE REACTIONS).

Ribavirin and INTRON A therapy should be suspended in patients with signs and symptoms of pancreatitis and discontinued in patients with confirmed pancreatitis.

Ribavirin should not be used in patients with creatinine clearance <50 mL/min. (See CLINICAL PHARMACOLOGY: Special Populations).

Pulmonary

Pulmonary symptoms, including dyspnea, pulmonary infiltrates, pneumonitis and pneumonia, have been reported during therapy with ribavirin/INTRON A; occasional cases of fatal pneumonia have occurred. In addition, sarcoidosis or the exacerbation of sarcoidosis has been reported. If there is evidence of pulmonary infiltrates or pulmonary function impairment, the patient should be closely monitored, and if appropriate, combination ribavirin/INTRON A treatment should be discontinued.

Dental and periodontal disorders have been reported in patients receiving ribavirin and interferon combination therapy. In addition, dry mouth could have a damaging effect on teeth and mucous membranes of the mouth during long-term treatment with the combination of ribavirin capsules and interferon alfa-2b. Patients should brush their teeth thoroughly twice daily and have regular dental examinations. In addition, some patients may experience vomiting. If this reaction occurs, they should be advised to rinse out their mouth thoroughly afterwards.

PRECAUTIONS

The safety and efficacy of ribavirin/INTRON A therapy for the treatment of HIV infection, adenovirus, RSV, parainfluenza, or influenza infections have not been established. Ribavirin capsules should not be used for these indications. Ribavirin for inhalation has a separate package insert, which should be consulted if ribavirin inhalation therapy is being considered.

The safety and efficacy of ribavirin/INTRON A therapy has not been established in liver or other organ transplant patients, patients with decompensated liver disease due to hepatitis C infection, patients who are nonresponders to interferon therapy, or patients coinfected with HBV or HIV.

Information for Patients

Patients must be informed that ribavirin capsules may cause birth defects and/or death of the exposed fetus. Ribavirin must not be used by women who are pregnant or by men whose female partners are pregnant. Extreme care must be taken to avoid pregnancy in female patients and in female partners of male patients taking ribavirin. Ribavirin should not be initiated until a report of a negative pregnancy test has been obtained immediately prior to initiation of therapy. Patients must perform a pregnancy test monthly during therapy and for 6 months posttherapy. Women of childbearing potential must be counseled about use of effective contraception (two reliable forms) prior to initiating therapy. Patients (male and female) must be advised of the teratogenic/embryocidal risks and must be instructed to practice effective contraception during ribavirin and for 6 months posttherapy. Patients (male and female) should be advised to notify the physician immediately in the event of a pregnancy. (See CONTRAINDICATIONSand WARNINGS).

If pregnancy does occur during treatment or during 6 months posttherapy, the patient must be advised of the teratogenic risk of ribavirin therapy to the fetus. Patients, or partners of patients, should immediately report any pregnancy that occurs during treatment or within 6 months after treatment cessation to their physician. Physicians should report such cases by calling the Ribavirin Pregnancy Registry at 1-800-593-2214.

Patients receiving ribavirin capsules should be informed of the benefits and risks associated with treatment, directed in its appropriate use, and referred to the patient MEDICATION GUIDE for ribavirin capsules. Patients should be informed that the effect of treatment of hepatitis C infection on transmission is not known, and that appropriate precautions to prevent transmission of the hepatitis C virus should be taken.

The most common adverse experience occurring with ribavirin capsules is anemia, which may be severe. (See ADVERSE REACTIONS). Patients should be advised that laboratory evaluations are required prior to starting therapy and periodically thereafter. (See Laboratory Tests). It is advised that patients be well hydrated, especially during the initial stages of treatment.

Laboratory Tests

The following laboratory tests are recommended for all patients treated with ribavirin capsules, prior to beginning treatment and then periodically thereafter.

- Standard hematologic tests – including hemoglobin (pretreatment, week 2 and week 4 of therapy, and as clinically appropriate [see WARNINGS]), complete and differential white blood cell counts, and platelet count.
- Blood chemistries – liver function tests and TSH.
- Pregnancy – including monthly monitoring for women of childbearing potential.
- ECG (See WARNINGS)

Carcinogenesis and Mutagenesis

Ribavirin did not cause an increase in any tumor type when administered for 6 months in the transgenic p53 deficient mouse model at doses up to 300 mg/kg (estimated human equivalent of 25 mg/kg based on body surface area adjustment for a 60 kg adult; approximately 1.9 times the maximum recommended human daily dose). Ribavirin was non-carcinogenic when administered for 2 years to rats at doses up to 40 mg/kg (estimated human equivalent of 5.71 mg/kg based on body surface area adjustment for a 60 kg adult). However, this dose was less than the maximum tolerated dose, and therefore the study was not adequate to fully characterize the carcinogenic potential of ribavirin.

Ribavirin demonstrated increased incidences of mutation and cell transformation in multiple genotoxicity assays. Ribavirin was active in the Balb/3T3 In Vitro Cell Transformation Assay. Mutagenic activity was observed in the mouse lymphoma assay, and at doses of 20 to 200 mg/kg (estimated human equivalent of 1.67 to 16.7 mg/kg, based on body surface area adjustment for a 60 kg adult; 0.1 to 1 times the maximum recommended human 24-hour dose of ribavirin) in a mouse micronucleus assay. A dominant lethal assay in rats was negative, indicating that if mutations occurred in rats they were not transmitted through male gametes.

Impairment of Fertility

Ribavirin demonstrated significant embryocidal and/or teratogenic effects at doses well below the recommended human dose in all animal species in which adequate studies have been conducted.

Fertile women and partners of fertile women should not receive ribavirin unless the patient and his/her partner are using effective contraception (two reliable forms). Based on a multiple dose half-life(t1/2) of ribavirin of 12 days, effective contraception must be utilized for 6 months posttherapy (e.g., 15 half-lives of clearance for ribavirin).

Ribavirin should be used with caution in fertile men. In studies in mice to evaluate the time course and reversibility of ribavirin-induced testicular degeneration at doses of 15 to 150 mg/kg/day (estimated human equivalent of 1.25 to 12.5 mg/kg/day, based on body surface area adjustment for a 60 kg adult; 0.1 to 0.8 times the maximum human 24-hour dose of ribavirin) administered for 3 or 6 months, abnormalities in sperm occurred. Upon cessation of treatment, essentially total recovery from ribavirin-induced testicular toxicity was apparent within 1 or 2 spermatogenesis cycles.

Animal Toxicology

Long-term studies in the mouse and rat (18 to 24 months; doses of 20 to 75 and 10 to 40 mg/kg/day, respectively {estimated human equivalent doses of 1.67 to 6.25 and 1.43 to 5.71 mg/kg/day, respectively, based on body surface area adjustment for a 60 kg adult; approximately 0.1 to 0.4 times the maximum human 24-hour dose of ribavirin}) have demonstrated a relationship between chronic ribavirin exposure and increased incidences of vascular lesions (microscopic hemorrhages) in mice. In rats, retinal degeneration occurred in controls, but the incidence was increased in ribavirin-treated rats.

Pregnancy Category X

(See CONTRAINDICATIONS.)

Ribavirin produced significant embryocidal and/or teratogenic effects in all animal species in which adequate studies have been conducted. Malformations of the skull, palate, eye, jaw, limbs, skeleton, and gastrointestinal tract were noted. The incidence and severity of teratogenic effects increased with escalation of the drug dose. Survival of fetuses and offspring was reduced. In conventional embryotoxicity/teratogenicity studies in rats and rabbits, observed no effect dose levels were well below those for proposed clinical use (0.3 mg/kg/day for both the rat and rabbit; approximately 0.06 times the recommended human 24-hour dose of ribavirin). No maternal toxicity or effects on offspring were observed in a peri/postnatal toxicity study in rats dosed orally at up to 1 mg/kg/day (estimated human equivalent dose of 0.17 mg/kg based on body surface area adjustment for a 60 kg adult; approximately 0.01 times the maximum recommended human 24-hour dose of ribavirin).

Potential Risk to the Fetus

Ribavirin is known to accumulate in intracellular components from where it is cleared very slowly. It is not known whether ribavirin contained in sperm will exert a potential teratogenic effect upon fertilization of the ova. In a study in rats, it was concluded that dominant lethality was not induced by ribavirin at doses up to 200 mg/kg for 5 days (estimated human equivalent doses of 7.14 to 28.6 mg/kg, based on body surface area adjustment for a 60 kg adult; up to 1.7 times the maximum recommended human dose of ribavirin). However, because of the potential human teratogenic effects of ribavirin, male patients should be advised to take every precaution to avoid risk of pregnancy for their female partners.

Women of childbearing potential should not receive ribavirin unless they are using effective contraception (two reliable forms) during the therapy period. In addition, effective contraception should be utilized for 6 months post-therapy based on a multiple-dose half-life (t1/2) of ribavirin of 12 days.

Male patients and their female partners must practice effective contraception (two reliable forms) during treatment with ribavirin and for the 6-month post-therapy period (e.g., 15 half-lives for ribavirin clearance from the body).

Ribavirin Pregnancy Registry

A Ribavirin Pregnancy Registry has been established to monitor maternal-fetal outcomes of pregnancies in female patients and female partners of male patients exposed to ribavirin during treatment and for six months following cessation of treatment. Physicians and patients are encouraged to report such cases by calling the Ribavirin Pregnancy Registry at 1-800-593-2214.

Nursing Mothers

It is not known whether the ribavirin product is excreted in human milk. Because of the potential for serious adverse reactions from the drug in nursing infants, a decision should be made whether to discontinue nursing or to delay or discontinue ribavirin capsules.

Geriatric Use

Clinical studies of ribavirin/INTRON A therapy did not include sufficient numbers of subjects aged 65 and over to determine if they respond differently from younger subjects.

Ribavirin is known to be substantially excreted by the kidney, and the risk of toxic reactions to this drug may be greater in patients with impaired renal function. Because elderly patients often have decreased renal function, care should be taken in dose selection. Renal function should be monitored and dosage adjustments should be made accordingly. Ribavirin should not be used in patients with creatinine clearance <50 mL/min. (See WARNINGS).

In general, ribavirin capsules should be administered to elderly patients cautiously, starting at the lower end of the dosing range, reflecting the greater frequency of decreased hepatic and/or cardiac function, and of concomitant disease or other drug therapy. In clinical trials, elderly subjects had a higher frequency of anemia (67%) than did younger patients (28%) (See WARNINGS).

Pediatric Use

Suicidal ideation or attempts occurred more frequently among pediatric patients, primarily adolescents, compared to adult patients (2.4% versus 1%) during treatment and off-therapy follow-up (see WARNINGS). As in adult patients, pediatric patients experienced other psychiatric adverse events (eg, depression, emotional lability, somnolence), anemia, and neutropenia (see WARNINGS). During a 48-week course of therapy there was a decrease in the rate of linear growth (mean percentile assignment decrease of 9%) and a decrease in the rate of weight gain (mean percentile assignment decrease of 13%). A general reversal of these trends was noted during the 24-week post-treatment period.

Didanosine

Co-administration of ribavirin capsules and didanosine is not recommended. Reports of fatal hepatic failure, as well as peripheral neuropathy, pancreatitis, and symptomatic hyperlactactemia/lactic acidosis have been reported in clinical trials (see CLINICAL PHARMACOLOGY: Drug Interactions).

Stavudine and Zidovudine

Ribavirin may antagonize the in vitro antiviral activity of stavudine and zidovudine against HIV. Therefore, concomitant use of ribavirin with either of these drugs should be used with caution (see CLINICAL PHARMACOLOGY: Drug Interactions).

ADVERSE REACTIONS

The primary toxicity of ribavirin is hemolytic anemia. Reductions in hemoglobin levels occurred within the first 1 to 2 weeks of oral therapy. (See WARNINGS). Cardiac and pulmonary events associated with anemia occurred in approximately 10% of patients (See WARNINGS).

Ribavirin/INTRON A Combination Therapy

In clinical trials, 19% and 6% of previously untreated and relapse patients, respectively, discontinued therapy due to adverse events in the combination arms compared to 13% and 3% in the interferon arms. Selected treatment-emergent adverse events that occurred in the US studies with ≥5% incidence are provided in TABLE 4 by treatment group. In general, the selected treatment-emergent adverse events were reported with lower incidence in the international studies as compared to the US studies with the exception of asthenia, influenza-like symptoms, nervousness, and pruritus.

TABLE 4. Selected Treatment-Emergent Adverse Events: Previously Untreated and Relapse Adult Patients
 | Percentage of Patients
 | US Previously Untreated Study |  |  |  | US Relapse Study
 | 24 weeks of treatment |  | 48 weeks of treatment |  | 24 weeks of treatment
Patients Reporting; Adverse Events [Patients reporting one or more adverse events. A patient may have reported more than one adverse event within a body system/organ class category.] | INTRON A; plus; Ribavirin; (N=228) | INTRON A; plus; Placebo; (N=231) | INTRON A; plus; Ribavirin; (N=228) | INTRON A; plus; Placebo; (N=225) | INTRON A; plus; Ribavirin; (N=77) | INTRON A; plus; Placebo; (N=76)
Application Site Disorders
Injection site inflammation | 13 | 10 | 12 | 14 | 6 | 8
Injection site reaction | 7 | 9 | 8 | 9 | 5 | 3
Body as a Whole –; General Disorders
Headache | 63 | 63 | 66 | 67 | 66 | 68
Fatigue | 68 | 62 | 70 | 72 | 60 | 53
Rigors | 40 | 32 | 42 | 39 | 43 | 37
Fever | 37 | 35 | 41 | 40 | 32 | 36
Influenza-like symptoms | 14 | 18 | 18 | 20 | 13 | 13
Asthenia | 9 | 4 | 9 | 9 | 10 | 4
Chest pain | 5 | 4 | 9 | 8 | 6 | 7
Central & Peripheral; Nervous System Disorders
Dizziness | 17 | 15 | 23 | 19 | 26 | 21
Gastrointestinal System Disorders
Nausea | 38 | 35 | 46 | 33 | 47 | 33
Anorexia | 27 | 16 | 25 | 19 | 21 | 14
Dyspepsia | 14 | 6 | 16 | 9 | 16 | 9
Vomiting | 11 | 10 | 9 | 13 | 12 | 8

TABLE 4. Selected Treatment-Emergent Adverse Events: Previously Untreated and Relapse Adult Patients (continued)
 | Percentage of Patients
 | US Previously Untreated Study |  |  |  | US Relapse Study
 | 24 weeks of treatment |  | 48 weeks of treatment |  | 24 weeks of treatment
Patients Reporting; Adverse Events [Patients reporting one or more adverse events. A patient may have reported more than one adverse event within a body system/organ class category.] | INTRON A; plus; Ribavirin; (N=228) | INTRON A; plus; Placebo; (N=231) | INTRON A; plus; Ribavirin; (N=228) | INTRON A; plus; Placebo; (N=225) | INTRON A; plus; Ribavirin; (N=77) | INTRON A; plus; Placebo; (N=76)
Musculoskeletal System Disorders
Myalgia | 61 | 57 | 64 | 63 | 61 | 58
Arthralgia | 30 | 27 | 33 | 36 | 29 | 29
Musculoskeletal pain | 20 | 26 | 28 | 32 | 22 | 28
Psychiatric Disorders
Insomnia | 39 | 27 | 39 | 30 | 26 | 25
Irritability | 23 | 19 | 32 | 27 | 25 | 20
Depression | 32 | 25 | 36 | 37 | 23 | 14
Emotional lability | 7 | 6 | 11 | 8 | 12 | 8
Concentration impaired | 11 | 14 | 14 | 14 | 10 | 12
Nervousness | 4 | 2 | 4 | 4 | 5 | 4
Respiratory System Disorders
Dyspnea | 19 | 9 | 18 | 10 | 17 | 12
Sinusitis | 9 | 7 | 10 | 14 | 12 | 7
Skin and Appendages Disorders
Alopecia | 28 | 27 | 32 | 28 | 27 | 26
Rash | 20 | 9 | 28 | 8 | 21 | 5
Pruritus | 21 | 9 | 19 | 8 | 13 | 4
Special Senses, Other Disorders
Taste perversion | 7 | 4 | 8 | 4 | 6 | 5

In addition, the following spontaneous adverse events have been reported during the marketing surveillance of ribavirin/INTRON A therapy: hearing disorder and vertigo.

Ribavirin/INTRON A Combination Therapy

Changes in selected hematologic values (hemoglobin, white blood cells, neutrophils, and platelets)during therapy are described below. (See TABLE 5).

Hemoglobin

Hemoglobin decreases among patients receiving ribavirin therapy began at Week 1, with stabilization by Week 4. In previously untreated patients treated for 48 weeks, the mean maximum decrease from baseline was 3.1 g/dL in the US study and 2.9 g/dL in the International study. In relapse patients, the mean maximum decrease from baseline was 2.8 g/dL in the US study and 2.6 g/dL in the international study. Hemoglobin values returned to pretreatment levels within 4 to 8 weeks of cessation of therapy in most patients.

Bilirubin and Uric Acid

Increases in both bilirubin and uric acid, associated with hemolysis, were noted in clinical trials. Most were moderate biochemical changes and were reversed within 4 weeks after treatment discontinuation. This observation occurs most frequently in patients with a previous diagnosis of Gilbert’s syndrome. This has not been associated with hepatic dysfunction or clinical morbidity.

TABLE 5. Selected Hematologic Values During Treatment with Ribavirin Capsules plus INTRON A: Previously Untreated and Relapse Adult Patients
 | Percentage of Patients
 | US Previously Untreated Study |  |  |  | US Relapse Study
 | 24 weeks of treatment |  | 48 weeks of treatment |  | 24 weeks of treatment
 | INTRON A; plus Ribavirin (N=228) | INTRON A; plus Placebo (N=231) | INTRON A; plus Ribavirin (N=228) | INTRON A; plus Placebo (N=225) | INTRON A; plus Ribavirin (N=77) | INTRON A; plus Placebo (N=76)
Hemoglobin (g/dL)
9.5-10.9 | 24 | 1 | 32 | 1 | 21 | 3
8.0-9.4 | 5 | 0 | 4 | 0 | 4 | 0
6.5-7.9 | 0 | 0 | 0 | 0.4 | 0 | 0
<6.5 | 0 | 0 | 0 | 0 | 0 | 0
Leukocytes (x10^9/L)
2.0-2.9 | 40 | 20 | 38 | 23 | 45 | 26
1.5-1.9 | 4 | 1 | 9 | 2 | 5 | 3
1.0-1.4 | 0.9 | 0 | 2 | 0 | 0 | 0
<1.0 | 0 | 0 | 0 | 0 | 0 | 0
Neutrophils (x10^9/L)
1.0-1.49 | 30 | 32 | 31 | 44 | 42 | 34
0.75-0.99 | 14 | 15 | 14 | 11 | 16 | 18
0.5-0.74 | 9 | 9 | 14 | 7 | 8 | 4
<0.5 | 11 | 8 | 11 | 5 | 5 | 8
Platelets (x10^9/L)
70-99 | 9 | 11 | 11 | 14 | 6 | 12
50-69 | 2 | 3 | 2 | 3 | 0 | 5
30-49 | 0 | 0.4 | 0 | 0.4 | 0 | 0
<30 | 0.9 | 0 | 1 | 0.9 | 0 | 0
Total Bilirubin (mg/dL)
1.5-3.0 | 27 | 13 | 32 | 13 | 21 | 7
3.1-6.0 | 0.9 | 0.4 | 2 | 0 | 3 | 0
6.1-12.0 | 0 | 0 | 0.4 | 0 | 0 | 0
>12.0 | 0 | 0 | 0 | 0 | 0 | 0

Postmarketing Experiences

The following adverse reactions have been identified during the post approval use of ribavirin capsules in combination with INTRON A: hearing disorder, vertigo, aplastic anemia and pure red cell aplasia. Because these reactions are reported voluntarily from a population of uncertain size, it is not always possible to reliably estimate their frequency or establish a causal relationship to drug exposure.

OVERDOSAGE

There is limited experience with overdosage. Acute ingestion of up to 20 grams of ribavirin capsules, INTRON A ingestion of up to 120 million units, and subcutaneous doses of INTRON A up to 10 times the recommended doses have been reported. Primary effects that have been observed are increased incidence and severity of the adverse events related to the therapeutic use of INTRON A and ribavirin. However, hepatic enzyme abnormalities, renal failure, hemorrhage, and myocardial infarction have been reported with administration of single subcutaneous doses of INTRON A that exceed dosing recommendations.

There is no specific antidote for INTRON A or ribavirin, and hemodialysis and peritoneal dialysis are not effective treatment of overdose of either agent.

DOSAGE AND ADMINISTRATION

(See CLINICAL PHARMACOLOGY: Special Populations; see WARNINGS.)

Adults

The recommended dose of ribavirin capsules in patients 18 years of age and older depends on the patient’s body weight. The recommended dose of ribavirin is provided in TABLE 6.

The recommended duration of treatment for patients previously untreated with interferon is 24 to 48 weeks. The duration of treatment should be individualized to the patient depending on baseline disease characteristics, response to therapy, and tolerability of the regimen. (See Description of Clinical Studies and ADVERSE REACTIONS). After 24 weeks of treatment, virologic response should be assessed. Treatment discontinuation should be considered in any patient who has not achieved an HCV RNA below the limit of detection of the assay by 24 weeks. There are no safety and efficacy data on treatment for longer than 48 weeks in the previously untreated patient population.

In patients who relapse following non-pegylated interferon mono-therapy, the recommended duration of treatment is 24 weeks. There are no safety and efficacy data on treatment for longer than 24 weeks in the relapse patient population.

TABLE 6. Recommended Dosing for Patients 18 years of age and older
Body Weight | Ribavirin Capsules
≤75 kg | 2 x 200 mg capsules AM,; 3 x 200 mg capsules PM; daily p.o.
>75 kg | 3 x 200 mg capsules AM,; 3 x 200 mg capsules PM; daily p.o.

Ribavirin may be administered without regard to food, but should be administered in a consistent manner with respect to food intake. (See CLINICAL PHARMACOLOGY).

Dose Modifications

(See TABLE 7.)

If severe adverse reactions or laboratory abnormalities develop during combination ribavirin/INTRON A therapy the dose should be modified, or discontinued if appropriate, until the adverse reactions abate. If intolerance persists after dose adjustment, ribavirin/INTRON A therapy should be discontinued.

Ribavirin should not be used in patients with creatinine clearance <50 mL/min. Subjects with impaired renal function and/or those over the age of 50 should be carefully monitored with respect to development of anemia. (See WARNINGSand CLINICAL PHARMACOLOGY: Special Populations).

Ribavirin should be administered with caution to patients with pre-existing cardiac disease. Patients should be assessed before commencement of therapy and should be appropriately monitored during therapy. If there is any deterioration of cardiovascular status, therapy should be stopped. (See WARNINGS).

For patients with a history of stable cardiovascular disease, a permanent dose reduction is required if the hemoglobin decreases by ≥2 g/dL during any 4-week period. In addition, for these cardiac history patients, if the hemoglobin remains <12 g/dL after 4 weeks on a reduced dose, the patient should discontinue combination ribavirin/INTRON A therapy.

It is recommended that a patient whose hemoglobin level falls below 10 g/dL have his/her ribavirin dose reduced to 600 mg daily (1 x 200 mg capsule AM, 2 x 200 mg capsules PM) for adults. A patient whose hemoglobin level falls below 8.5 g/dL should be permanently discontinued from ribavirin therapy. (See WARNINGS).

TABLE 7. Guidelines for Dose Modifications and Discontinuation for Anemia
 | Dose Reduction; Ribavirin –; 600 mg daily adults | Permanent; Discontinuation of; Ribavirin Treatment
Hemoglobin
No Cardiac History | <10 g/dL | <8.5 g/dL
Cardiac History Patients | ≥2 g/dL decrease; during any 4-week; period during treatment | <12 g/dL after; 4 weeks dose; reduction

HOW SUPPLIED

Ribavirin capsules, 200 mg are white, opaque, hard gelatin capsules imprinted (in blue) RIBAVIRIN over 200 mg on cap and GG 608 on body, and are supplied as follows:

NDC 0781-2043-42 in bottles of 42 capsules

NDC 0781-2043-16 in bottles of 56 capsules

NDC 0781-2043-67 in bottles of 70 capsules

NDC 0781-2043-04 in bottles of 84 capsules

NDC 0781-2043-01 in bottles of 100 capsules

NDC 0781-2043-28 in bottles of 168 capsules

NDC 0781-2043-10 in bottles of 1000 capsules

NDC 0781-2043-13 in unit dose packages of 100 capsules

Dispense in a tight container as defined in the USP.

Store at 25°C (77°F); excursions permitted to 15°-30°C (59°-86°F) [see USP Controlled Room Temperature].

APPENDIX to Package Insert (Information on Ribavirin Capsules taken together with INTRON A)

[Note: In addition to REBETOL® (ribavirin) Capsules, Schering Corporation also markets REBETRON®. REBETRON is a copackaged combination therapy containing REBETOL (ribavirin, USP) and INTRON A (interferon alfa-2b, recombinant) Injection. REBETRON has a package insert that provides information on the combination use of REBETOL (ribavirin, USP) and INTRON A. This Appendix provides information on ribavirin capsules taken together with INTRON A that corresponds to information in the package insert for REBETRON.]

BOXED WARNING

CONTRAINDICATIONS AND WARNINGS

Combination ribavirin capsules/INTRON A therapy is contraindicated in females who are pregnant and in the male partners of females who are pregnant. Extreme care must be taken to avoid pregnancy during therapy and for 6 months after completion of treatment in female patients, and in female partners of male patients who are taking combination ribavirin capsules/INTRON A therapy. Females of childbearing potential and males must use two reliable forms of effective contraception during treatment and during the 6-month posttreatment follow-up period. Significant teratogenic and/or embryocidal effects have been demonstrated for ribavirin in all animal species studied. See CONTRAINDICATIONS and WARNINGS.

Ribavirin capsules monotherapy is not effective for the treatment of chronic hepatitis C and should not be used for this indication. See WARNINGS.

Alpha interferons, including INTRON A, cause or aggravate fatal or life-threatening neuropsychiatric, autoimmune, ischemic, and infectious disorders. Patients should be monitored closely with periodic clinical and laboratory evaluations. Patients with persistently severe or worsening signs or symptoms of these conditions should be withdrawn from therapy. In many but not all cases these disorders resolve after stopping INTRON A therapy. See WARNINGSand ADVERSE REACTIONS.

DESCRIPTION

Ribavirin Capsules

Ribavirin is a nucleoside analog with antiviral activity. The chemical name of ribavirin is 1-β-D-ribofuranosyl-1H-1,2,4-triazole-3-carboxamide and has the following structural formula:

Ribavirin is a white, crystalline powder. It is freely soluble in water and slightly soluble in anhydrous alcohol. The molecular formula is C8H12N4O5 and the molecular weight is 244.21.

Ribavirin capsules consist of white powder in a white, opaque, gelatin capsule. Each capsule, for oral administration, contains 200 mg ribavirin. In addition, each capsule contains the following inactive ingredients: croscarmellose sodium, hypromellose, magnesium stearate, mannitol and povidone. The capsule shell consists of gelatin and titanium dioxide. The capsule is printed with edible blue pharmaceutical ink which is made of FD&C Blue #2 aluminum lake, propylene glycol, shellac and titanium dioxide.

INTRON A

INTRON A is Schering Corporation’s brand name for interferon alfa-2b, recombinant, a purified, sterile, recombinant interferon product.

Interferon alfa-2b, recombinant has been classified as an alpha interferon and is a water-soluble protein composed of 165 amino acids with a molecular weight of 19,271 daltons produced by recombinant DNA techniques. It is obtained from the bacterial fermentation of a strain of Escherichia coli bearing a genetically engineered plasmid containing an interferon alfa-2b gene from human leukocytes. The fermentation is carried out in a defined nutrient medium containing the antibiotic tetracycline hydrochloride at a concentration of 5 to 10 mg/L; the presence of this antibiotic is not detectable in the final product.

INTRON A Injection is a clear, colorless solution. The 3 million IU vial of INTRON A Injection contains 3 million IU of interferon alfa-2b, recombinant per 0.5 mL. The 18 million IU multidose vial of INTRON A Injection contains a total of 22.8 million IU of interferon alfa-2b, recombinant per 3.8 mL (3 million IU/0.5 mL) in order to provide the delivery of six 0.5 mL doses, each containing 3 million IU of INTRON A (for a label strength of 18 million IU). The 18 million IU INTRON A Injection multidose pen contains a total of 22.5 million IU of interferon alfa-2b, recombinant per 1.5 mL (3 million IU/0.2 mL) in order to provide the delivery of six 0.2-mL doses, each containing 3 million IU of INTRON A (for a label strength of 18 million IU). Each mL also contains 7.5 mg sodium chloride, 1.8 mg sodium phosphate dibasic, 1.3 mg sodium phosphate monobasic, 0.1 mg edetate disodium, 0.1 mg polysorbate 80, and 1.5 mg m-cresol as a preservative.

Based on the specific activity of approximately 2.6 x 10^8 IU/mg protein as measured by HPLC assay, the corresponding quantities of interferon alfa-2b, recombinant in the vials and pen described above are approximately 0.012 mg, 0.088 mg, and 0.087 mg protein, respectively.

Ribavirin/Interferon alfa-2b, recombinant

The mechanism of inhibition of hepatitis C virus (HCV) RNA by combination therapy with ribavirin capsules and INTRON A has not been established.

CLINICAL PHARMACOLOGY

Interferon alfa-2b, recombinant

Single- and multiple-dose pharmacokinetic properties of INTRON A (interferon alfa-2b, recombinant) are summarized in TABLE 1. Following a single 3 million IU (MIU) subcutaneous dose in 12 patients with chronic hepatitis C, mean (% CV [In this section of the label, numbers in parenthesis indicate % coefficient of variation.]) serum concentrations peaked at 7 (44%) hours. Following 4 weeks of subcutaneous dosing with 3 MIU three times a week (TIW), interferon serum concentrations were undetectable predose. However, a twofold increase in bioavailability was noted upon multiple dosing of interferon; the reason for this is unknown. Mean half-life values following single- and multiple-dose administrations were 6.8 (24%) hours and 6.5 (29%) hours, respectively.

Ribavirin

Single- and multiple-dose pharmacokinetic properties in adults with chronic hepatitis C are summarized in TABLE 1. Ribavirin was rapidly and extensively absorbed following oral administration. However, due to first-pass metabolism, the absolute bioavailability averaged 64% (44%). There was a linear relationship between dose and AUCtf (AUC from time zero to last measurable concentration) following single doses of 200 to 1200 mg ribavirin. The relationship between dose and Cmax was curvilinear, tending to asymptote above single doses of 400 to 600 mg.

Upon multiple oral dosing, based on AUC12hr, a sixfold accumulation of ribavirin was observed in plasma. Following oral dosing with 600 mg BID, steady-state was reached by approximately 4 weeks, with mean steady-state plasma concentrations of 2200 (37%) ng/mL. Upon discontinuation of dosing, the mean half-life was 298 (30%) hours, which probably reflects slow elimination from nonplasma compartments.

Effect of Food on Absorption of Ribavirin

Both AUCtf and Cmax increased by 70% when ribavirin capsules were administered with a high-fat meal (841 kcal, 53.8 g fat, 31.6 g protein, and 57.4 g carbohydrate) in a single-dose pharmacokinetic study. There are insufficient data to address the clinical relevance of these results. Clinical efficacy studies were conducted without instructions with respect to food consumption. (See DOSAGE AND ADMINISTRATION.)

Effect of Antacid on Absorption of Ribavirin

Coadministration with an antacid containing magnesium, aluminum, and simethicone (Mylanta®) resulted in a 14% decrease in mean ribavirin AUCtf. The clinical relevance of results from this single-dose study is unknown.

TABLE 1. Mean (% CV) Pharmacokinetic Parameters for INTRON A and RIBAVIRIN CAPSULES When Administered Individually to Adults with Chronic Hepatitis C
 | INTRON A (N=12) |  | Ribavirin Capsules; (N=12)
Parameter | Single; Dose; 3 MIU | Multiple; Dose; 3 MIU; TIW | Single; Dose; 600 mg | Multiple; Dose; 600 mg BID
Tmax (hr) | 7 (44) | 5 (37) | 1.7 (46) [N=11] | 3 (60)
Cmax [IU/mL for INTRON A and ng/mL for RIBAVIRIN CAPSULES] | 13.9 (32) | 29.7 (33) | 782 (37) | 3680 (85)
AUCtf [IU•hr/mL for INTRON A and ng•hr/mL for RIBAVIRIN CAPSULES] | 142 (43) | 333 (39) | 13400 (48) | 228000 (25)
T1/2 (hr) | 6.8 (24) | 6.5 (29) | 43.6 (47) | 298 (30)
Apparent
Volume of
Distribution (L) |  |  | 2825 (9) [data obtained from a single-dose pharmacokinetic study using ^14C labeled ribavirin; N=5]
Apparent; Clearance (L/hr) | 14.3 (17) |  | 38.2 (40)
Absolute; Bioavailability |  |  | 64% (44) [N=6]

Ribavirin transport into nonplasma compartments has been most extensively studied in red blood cells, and has been identified to be primarily via an es-type equilibrative nucleoside transporter. This type of transporter is present on virtually all cell types and may account for the extensive volume of distribution. Ribavirin does not bind to plasma proteins.

Ribavirin has two pathways of metabolism: (i) a reversible phosphorylation pathway in nucleated cells; and (ii) a degradative pathway involving deribosylation and amide hydrolysis to yield a triazole carboxylic acid metabolite. Ribavirin and its triazole carboxamide and triazole carboxylic acid metabolites are excreted renally. After oral administration of 600 mg of ^14C-ribavirin, approximately 61% and 12% of the radioactivity was eliminated in the urine and feces, respectively, in 336 hours. Unchanged ribavirin accounted for 17% of the administered dose.

Results of in vitro studies using both human and rat liver microsome preparations indicated little or no cytochrome P450 enzyme-mediated metabolism of ribavirin, with minimal potential for P450 enzyme-based drug interactions.

No pharmacokinetic interactions were noted between INTRON A Injection and ribavirin capsules in a multiple-dose pharmacokinetic study.

Renal Dysfunction

The pharmacokinetics of ribavirin were assessed after administration of a single oral dose (400 mg) of ribavirin to subjects with varying degrees of renal dysfunction. The mean AUCtf value was threefold greater in subjects with creatinine clearance values between 10 to 30 mL/min when compared to control subjects (creatinine clearance >90 mL/min). This appears to be due to reduction of apparent clearance in these patients. Ribavirin was not removed by hemodialysis. Patients with creatinine clearance < 50 mL/min should not be treated with ribavirin capsules (see WARNINGS).

Hepatic Dysfunction

The effect of hepatic dysfunction was assessed after a single oral dose of ribavirin (600 mg). The mean AUCtf values were not significantly different in subjects with mild, moderate, or severe hepatic dysfunction (Child-Pugh Classification A, B, or C), when compared to control subjects. However, the mean Cmax values increased with severity of hepatic dysfunction and was twofold greater in subjects with severe hepatic dysfunction when compared to control subjects.

Elderly Patients

Pharmacokinetic evaluations for elderly subjects have not been performed.

Gender

There were no clinically significant pharmacokinetic differences noted in a single-dose study of eighteen male and eighteen female subjects.

Drug Interactions

Ribavirin has been shown in vitro to inhibit phosphorylation of zidovudine and stavudine which could lead to decreased antiretroviral activity. Exposure to didanosine or its active metabolite (dideoxyadenosine 5’-triphosphate) is increased when didanosine is coadministered with ribavirin, which could cause or worsen clinical toxicities (see PRECAUTIONS: Drug Interactions).

INDICATIONS AND USAGE

Ribavirin capsules are indicated in combination with INTRON A (interferon alfa-2b, recombinant) Injection for the treatment of chronic hepatitis C in patients 18 years of age and older with compensated liver disease previously untreated with alpha interferon or in patients 18 years of age and older who have relapsed following alpha interferon therapy.

The safety and efficacy of ribavirin capsules with non-pegylated interferons other than the INTRON A product have not been established.

Previously Untreated Patients

Adults with compensated chronic hepatitis C and detectable HCV RNA (assessed by a central laboratory using a research-based RT-PCR assay) who were previously untreated with alpha interferon therapy were enrolled into two multicenter, double-blind trials (US and International) and randomized to receive ribavirin capsules 1200 mg/day (1000 mg/day for patients weighing ≤75 kg) plus INTRON A Injection 3 MIU TIW or INTRON A Injection plus placebo for 24 or 48 weeks followed by 24 weeks of off-therapy follow-up. The International study did not contain a 24-week INTRON A plus placebo treatment arm. The US study enrolled 912 patients who, at baseline, were 67% male, 89% caucasian with a mean Knodell HAI score (I+II+III) of 7.5, and 72% genotype 1. The International study, conducted in Europe, Israel, Canada, and Australia, enrolled 799 patients (65% male, 95% caucasian, mean Knodell score 6.8, and 58% genotype 1).

Study results are summarized in TABLE 2.

TABLE 2. Virologic and Histologic Responses: Previously Untreated Patients [Number (%) of patients.]
 | US Study |  |  |  | International Study
 | 24 weeks of treatment |  | 48 weeks of treatment |  | 24 weeks of; treatment | 48 weeks of treatment
 | INTRON A; plus; Ribavirin; capsules; (N=228) | INTRON A; plus; Placebo; (N=231) | INTRON A; plus; Ribavirin; capsules; (N=228) | INTRON A; plus; Placebo; (N=225) | INTRON A; plus; Ribavirin; capsules; (N=265) | INTRON A; plus; Ribavirin; capsules; (N=268) | INTRON A; plus; Placebo; (N=266)
Virologic; Response
Responder [Defined as HCV RNA below limit of detection using a research based RT-PCR assay at end of treatment and during follow-up period.] | 65 (29) | 13 (6) | 85 (37) | 27 (12) | 86 (32) | 113 (42) | 46 (17)
Nonresponder | 147 (64) | 194 (84) | 110 (48) | 168 (75) | 158 (60) | 120 (45) | 196 (74)
Missing Data | 16 (7) | 24 (10) | 33 (14) | 30 (13) | 21 (8) | 35 (13) | 24 (9)
Histologic; Response
Improvement [Defined as posttreatment (end of follow-up) minus pretreatment liver biopsy Knodell HAI score (I+II+III) improvement of ≥2 points.] | 102 (45) | 77 (33) | 96 (42) | 65 (29) | 103 (39) | 102 (38) | 69 (26)
No improvement | 77 (34) | 99 (43) | 61 (27) | 93 (41) | 85 (32) | 58 (22) | 111 (41)
Missing Data | 49 (21) | 55 (24) | 71 (31) | 67 (30) | 77 (29) | 108 (40) | 86 (32)

Of patients who had not achieved HCV RNA below the limit of detection of the research based assay by week 24 of ribavirin capsules/INTRON A treatment, less than 5% responded to an additional 24 weeks of combination treatment.

Among patients with HCV genotype 1 treated with ribavirin capsules/INTRON A therapy who achieved HCV RNA below the detection limit of the research-based assay by 24 weeks, those randomized to 48 weeks of treatment had higher virologic responses compared to those in the 24-week treatment group. There was no observed increase in response rates for patients with HCV nongenotype 1 randomized to ribavirin capsules/INTRON A therapy for 48 weeks compared to 24 weeks.

Relapse Patients

Patients with compensated chronic hepatitis C and detectable HCV RNA (assessed by a central laboratory using a research based RT-PCR assay) who had relapsed following one or two courses of interferon therapy (defined as abnormal serum ALT levels) were enrolled into two multicenter, double-blind trials (US and International) and randomized to receive ribavirin capsules 1200 mg/day (1000 mg/day for patients weighing ≤75 kg) plus INTRON A 3 MIU TIW or INTRON A plus placebo for 24 weeks followed by 24 weeks of off-therapy follow-up. The US study enrolled 153 patients who, at baseline, were 67% male, 92% caucasian with a mean Knodell HAI score (I+II+III) of 6.8, and 58% genotype 1. The International study, conducted in Europe, Israel, Canada, and Australia, enrolled 192 patients (64% male, 95% caucasian, mean Knodell score 6.6, and 56% genotype 1).

Study results are summarized in TABLE 3.

TABLE 3. Virologic and Histologic Responses: Relapse Patients [Number (%) of patients.]
 | US Study |  | International Study
 | INTRON A; plus; Ribavirin; capsules; (N=77) | INTRON A; plus; Placebo; (N=76) | INTRON A; plus; Ribavirin; capsules; (N=96) | INTRON A; plus; Placebo; (N=96)
Virologic; Response
Responder [Defined as HCV RNA below limit of detection using a research based RT-PCR assay at end of treatment and during follow-up period.] | 33 (43) | 3 (4) | 46 (48) | 5 (5)
Nonresponder | 36 (47) | 66 (87) | 45 (47) | 91 (95)
Missing Data | 8 (10) | 7 (9) | 5 (5) | 0 (0)
Histologic; Response
Improvement [Defined as posttreatment (end of follow-up) minus pretreatment liver biopsy Knodell HAI score (I+II+III) improvement of ≥2 points.] | 38 (49) | 27 (36) | 49 (51) | 30 (31)
No improvement | 23 (30) | 37 (49) | 29 (30) | 44 (46)
Missing Data | 16 (21) | 12 (16) | 18 (19) | 22 (23)

Virologic and histologic responses were similar among male and female patients in both the previously untreated and relapse studies.

CONTRAINDICATIONS

Combination ribavirin capsules/INTRON A therapy must not be used by females who are pregnant or by males whose female partners are pregnant. Extreme care must be taken to avoid pregnancy in female patients and in female partners of male patients taking combination ribavirin capsules/INTRON A therapy. Combination ribavirin capsules/INTRON A therapy should not be initiated until a report of a negative pregnancy test has been obtained immediately prior to initiation of therapy. Females of childbearing potential and males must use two forms of effective contraception during treatment and during the 6 months after treatment has been concluded. Significant teratogenic and/or embryocidal effects have been demonstrated for ribavirin in all animal species in which adequate studies have been conducted. These effects occurred at doses as low as one twentieth of the recommended human dose of ribavirin capsules. If pregnancy occurs in a patient or partner of a patient during treatment or during the 6 months after treatment stops, physicians are encouraged to report such cases by calling the Ribavirin Pregnancy Registry at 1-800-593-2214. See boxed CONTRAINDICATIONS AND WARNINGS. See WARNINGS.

Ribavirin capsules in combination with INTRON A Injection is contraindicated in patients with a history of hypersensitivity to ribavirin and/or alpha interferon or any component of the capsule and/or injection.

Patients with autoimmune hepatitis must not be treated with combination ribavirin capsules/INTRON A therapy.

WARNINGS

Pregnancy

Category X, may cause birth defects. See boxed CONTRAINDICATIONS AND WARNINGS. See CONTRAINDICATIONS.

Anemia

HEMOLYTIC ANEMIA (HEMOGLOBIN <10 G/DL) WAS OBSERVED IN APPROXIMATELY 10% OF RIBAVIRIN CAPSULES/INTRON A-TREATED PATIENTS IN CLINICAL TRIALS (See ADVERSE REACTIONS: Laboratory Values: Hemoglobin). ANEMIA OCCURRED WITHIN 1 TO 2 WEEKS OF INITIATION OF RIBAVIRIN THERAPY. BECAUSE OF THIS INITIAL ACUTE DROP IN HEMOGLOBIN, IT IS ADVISED THAT COMPLETE BLOOD COUNTS (CBC) SHOULD BE OBTAINED PRETREATMENT AND AT WEEK 2 AND WEEK 4 OF THERAPY OR MORE FREQUENTLY IF CLINICALLY INDICATED. PATIENTS SHOULD THEN BE FOLLOWED AS CLINICALLY APPROPRIATE.

The anemia associated with ribavirin capsules/INTRON A therapy may result in deterioration of cardiac function and/or exacerbation of the symptoms of coronary disease. Patients should be assessed before initiation of therapy and should be appropriately monitored during therapy. If there is any deterioration of cardiovascular status, therapy should be suspended or discontinued. (See DOSAGE AND ADMINISTRATION.) Because cardiac disease may be worsened by drug induced anemia, patients with a history of significant or unstable cardiac disease should not use combination ribavirin capsules/INTRON A therapy. (See ADVERSE REACTIONS.)

Similarly, patients with hemoglobinopathies (e.g., thalassemia, sickle-cell anemia) should not be treated with combination ribavirin capsules/INTRON A therapy.

Psychiatric

Severe psychiatric adverse events, including depression, psychoses, aggressive behavior, hallucinations, violent behavior (suicidal ideation, suicidal attempts, suicides) and rare instances of homicidal ideation have occurred during combination ribavirin capsules/Intron A therapy, both in patients with and without a previous psychiatric disorder. Ribavirin capsules/Intron A therapy should be used with extreme caution in patients with a history of pre-existing psychiatric disorders, and all patients should be carefully monitored for evidence of depression and other psychiatric symptoms.

Suspension of ribavirin capsules/Intron A therapy should be considered if psychiatric intervention and/or dose reduction is unsuccessful in controlling psychiatric symptoms. In severe cases, therapy should be stopped immediately and psychiatric intervention sought. (See ADVERSE REACTIONS.)

Bone Marrow Toxicity

INTRON A therapy suppresses bone marrow function and may result in severe cytopenias including very rare events of aplastic anemia. It is advised that complete blood counts (CBC) be obtained pretreatment and monitored routinely during therapy (see PRECAUTIONS: Laboratory Tests). INTRON A therapy should be discontinued in patients who develop severe decreases in neutrophil (<0.5 x 10^9/L) or platelet counts (<25 x 10^9/L) (see DOSAGE AND ADMINISTRATION: Guidelines for Dose Modifications).

Pulmonary

Pulmonary symptoms, including dyspnea, pulmonary infiltrates, pneumonitis and pneumonia, have been reported during therapy with ribavirin capsules/INTRON A; occasional cases of fatal pneumonia have occurred. In addition, sarcoidosis or the exacerbation of sarcoidosis has been reported. If there is evidence of pulmonary infiltrates or pulmonary function impairment, the patient should be closely monitored, and if appropriate, combination ribavirin capsules/INTRON A treatment should be discontinued.

Other

- Ribavirin capsules monotherapy is not effective for the treatment of chronic hepatitis C and should not be used for this indication.
- Fatal and nonfatal pancreatitis has been observed in patients treated with ribavirin capsules/INTRON A therapy. Ribavirin capsules/INTRON A therapy should be suspended in patients with signs and symptoms of pancreatitis and discontinued in patients with confirmed pancreatitis.
- Combination ribavirin capsules/INTRON A therapy should not be used in patients with creatinine clearance <50 mL/min.
- Diabetes mellitus and hyperglycemia have been observed in patients treated with INTRON A.
- Ophthalmologic disorders have been reported with treatment with alpha interferons (including INTRON A therapy). Investigators using alpha interferons have reported the occurrence of retinal hemorrhages, cotton wool spots, and retinal artery or vein obstruction in rare instances. Any patient complaining of loss of visual acuity or visual field should have an eye examination. Because these ocular events may occur in conjunction with other disease states, a visual exam prior to initiation of combination ribavirin capsules/INTRON A therapy is recommended in patients with diabetes mellitus or hypertension.
- Acute serious hypersensitivity reactions (eg, urticaria, angioedema, bronchoconstriction, anaphylaxis) have been observed in INTRON A-treated patients; if such an acute reaction develops, combination ribavirin capsules/INTRON A therapy should be discontinued immediately and appropriate medical therapy instituted.
- Combination ribavirin capsules/INTRON A therapy should be discontinued for patients developing thyroid abnormalities during treatment whose thyroid function cannot be controlled by medication.

PRECAUTIONS

Exacerbation of autoimmune disease has been reported in patients receiving alpha interferon therapy (including INTRON A therapy). Ribavirin capsules/INTRON A therapy should be used with caution in patients with other autoimmune disorders.

There have been reports of interferon, including INTRON A (interferon alfa-2b, recombinant) exacerbating pre-existing psoriasis; therefore, combination ribavirin capsules/INTRON A therapy should be used in these patients only if the potential benefit justifies the potential risk.

The safety and efficacy of ribavirin capsules/INTRON A therapy has not been established in liver or other organ transplant patients, decompensated hepatitis C patients, patients who are nonresponders to interferon therapy, or patients coinfected with HBV or HIV.

The safety and efficacy of ribavirin capsules monotherapy for the treatment of HIV infection, adenovirus, early RSV infection, parainfluenza, or influenza have not been established and ribavirin capsules should not be used for these indications.

There is no information regarding the use of ribavirin capsules with other interferons.

Triglycerides

Elevated triglyceride levels have been observed in patients treated with interferon including ribavirin capsules/INTRON A therapy. Elevated triglyceride levels should be managed as clinically appropriate. Severe hypertriglyceridemia (triglycerides >1000 mg/dL) may result in pancreatitis. Discontinuation of ribavirin capsules/INTRON A therapy should be considered for patients with persistently elevated triglycerides (triglycerides >1000 mg/dL) associated with symptoms of potential pancreatitis, such as abdominal pain, nausea, or vomiting (see WARNINGS: Other).

Nucleoside Analogs

Administration of nucleoside analogues has resulted in fatal and nonfatal lactic acidosis. Coadministration of ribavirin and nucleoside analogues should be undertaken with caution and only if the potential benefit outweighs the potential risks.

Information for Patients

Combination ribavirin capsules/INTRON A therapy must not be used by females who are pregnant or by males whose female partners are pregnant. Extreme care must be taken to avoid pregnancy in female patients and in female partners of male patients taking combination ribavirin capsules/INTRON A therapy. Combination ribavirin capsules/INTRON A therapy should not be initiated until a report of a negative pregnancy test has been obtained immediately prior to initiation of therapy. Patients must perform a pregnancy test monthly during therapy and for 6 months posttherapy. Females of childbearing potential must be counseled about use of effective contraception (two reliable forms) prior to initiating therapy. Patients (male and female) must be advised of the teratogenic/embryocidal risks and must be instructed to practice effective contraception during combination ribavirin capsules/INTRON A therapy and for 6 months posttherapy. Patients (male and female) should be advised to notify the physician immediately in the event of a pregnancy. (See CONTRAINDICATIONS).

If pregnancy does occur during treatment or during 6 months posttherapy, the patient must be advised of the significant teratogenic risk of ribavirin capsules therapy to the fetus. Patients, or partners of patients, should immediately report any pregnancy that occurs during treatment or within 6 months after treatment cessation to their physician. Physicians are encouraged to report such cases by calling the Ribavirin Pregnancy Registry at 1-800-593-2214.

Patients receiving combination ribavirin capsules/INTRON A treatment should be directed in its appropriate use, informed of the benefits and risks associated with treatment, and referred to the Appendix of the Medication Guide on ribavirin capsules. There are no data evaluating whether ribavirin capsules/INTRON A therapy will prevent transmission of infection to others. Also, it is not known if treatment with ribavirin capsules/INTRON A therapy will cure hepatitis C or prevent cirrhosis, liver failure, or liver cancer that may be the result of infection with the hepatitis C virus.

If home use is prescribed, a puncture-resistant container for the disposal of used syringes and needles should be supplied to the patient. Patients should be thoroughly instructed in the importance of proper disposal and cautioned against any reuse of needles and syringes. The full container should be disposed of according to the directions provided by the physician. [see Appendix to the Medication Guide on ribavirin capsules.] To avoid possible transmission of disease, do not share your multidose pen with anyone; it is for you and you alone.

The most common adverse experiences occurring with combination ribavirin capsules/INTRON A therapy are “flu-like” symptoms, such as headache, fatigue, myalgia, and fever (see ADVERSE REACTIONS) and appear to decrease in severity as treatment continues. Some of these “flu-like” symptoms may be minimized by bedtime administration of INTRON A therapy. Antipyretics should be considered to prevent or partially alleviate the fever and headache. Another common adverse experience associated with INTRON A therapy is thinning of the hair.

Patients should be advised that laboratory evaluations are required prior to starting therapy and periodically thereafter (see Laboratory Tests). It is advised that patients be well hydrated, especially during the initial stages of treatment.

Laboratory Tests

The following laboratory tests are recommended for all patients on combination ribavirin capsules/INTRON A therapy, prior to beginning treatment and then periodically thereafter.

- Standard hematologic tests – including hemoglobin (pretreatment, week 2 and week 4 of therapy, and as clinically appropriate [see WARNINGS]), complete and differential white blood cell counts, and platelet count.
- Blood chemistries – liver function tests and TSH.
- Pregnancy – including monthly monitoring for females of child bearing potential.

Carcinogenesis and Mutagenesis

Carcinogenicity studies with interferon alfa-2b, recombinant have not been performed because neutralizing activity appears in the serum after multiple dosing in all of the animal species tested.

Ribavirin did not cause an increase in any tumor type when administered for 6 months in the transgenic p53 deficient mouse model at doses up to 300 mg/kg (estimated human equivalent of 25 mg/kg based on body surface area adjustment for a 60 kg adult; approximately 1.9 times the maximum recommended human daily dose). Ribavirin was non-carcinogenic when administered for 2 years to rats at doses up to 40 mg/kg (estimated human equivalent of 5.71 mg/kg based on body surface area adjustment for a 60 kg adult). However, this dose was less than the maximum tolerated dose, and therefore the study was not adequate to fully characterize the carcinogenic potential of ribavirin.

Mutagenicity studies have demonstrated that interferon alfa-2b, recombinant is not mutagenic. Ribavirin demonstrated increased incidences of mutation and cell transformation in multiple genotoxicity assays. Ribavirin was active in the Balb/3T3 In Vitro Cell Transformation Assay. Mutagenic activity was observed in the mouse lymphoma assay, and at doses of 20 to 200 mg/kg (estimated human equivalent of 1.67 to 16.7 mg/kg, based on body surface area adjustment for a 60 kg adult; 0.1 to 1 times the maximum recommended human 24-hour dose of ribavirin) in a mouse micronucleus assay. A dominant lethal assay in rats was negative, indicating that if mutations occurred in rats they were not transmitted through male gametes.

Impairment of Fertility

No reproductive toxicology studies have been performed using interferon alfa-2b, recombinant in combination with ribavirin. However, evidence provided below for interferon alfa-2b, recombinant and ribavirin when administered alone indicate that both agents have adverse effects on reproduction. It should be assumed that the effects produced by either agent alone will also be caused by the combination of the two agents. Interferons may impair human fertility. In studies of interferon alfa-2b recombinant administration in nonhuman primates, menstrual cycle abnormalities have been observed. Decreases in serum estradiol and progesterone concentrations have been reported in females treated with human leukocyte interferon. In addition, ribavirin demonstrated significant embryocidal and/or teratogenic effects at doses well below the recommended human dose in all animal species in which adequate studies have been conducted.

Fertile females and partners of fertile females should not receive combination ribavirin capsules/INTRON A therapy unless the patient and his/her partner are using effective contraception (two reliable forms). Based on a multiple dose half-life (t1/2) of ribavirin of 12 days, effective contraception must be utilized for 6 months posttherapy (e.g., 15 half-lives of clearance for ribavirin).

Combination ribavirin capsules/INTRON A therapy should be used with caution in fertile males. In studies in mice to evaluate the time course and reversibility of ribavirin-induced testicular degeneration at doses of 15 to 150 mg/kg/day (estimated human equivalent of 1.25 to 12.5 mg/kg/day, based on body surface area adjustment for a 60 kg adult; 0.1 to 0.8 times the maximum human 24-hour dose of ribavirin) administered for 3 or 6 months, abnormalities in sperm occurred. Upon cessation of treatment, essentially total recovery from ribavirin-induced testicular toxicity was apparent within 1 or 2 spermatogenesis cycles.

Animal Toxicology

Long-term studies in the mouse and rat (18 to 24 months; doses of 20 to 75 and 10 to 40 mg/kg/day, respectively [estimated human equivalent doses of 1.67 to 6.25 and 1.43 to 5.71 mg/kg/day, respectively, based on body surface area adjustment for a 60 kg adult; approximately 0.1 to 0.4 times the maximum human 24-hour dose of ribavirin]) have demonstrated a relationship between chronic ribavirin exposure and increased incidences of vascular lesions (microscopic hemorrhages) in mice. In rats, retinal degeneration occurred in controls, but the incidence was increased in ribavirin-treated rats.

Pregnancy Category X:

(See CONTRAINDICATIONS.)

Interferon alfa-2b, recombinant has been shown to have abortifacient effects in Macaca mulatta (rhesus monkeys) at 15 and 30 million IU/kg (estimated human equivalent of 5 and 10 million IU/kg, based on body surface area adjustment for a 60 kg adult). There are no adequate and well-controlled studies in pregnant females.

Ribavirin produced significant embryocidal and/or teratogenic effects in all animal species in which adequate studies have been conducted. Malformations of the skull, palate, eye, jaw, limbs, skeleton, and gastrointestinal tract were noted. The incidence and severity of teratogenic effects increased with escalation of the drug dose. Survival of fetuses and offspring was reduced. In conventional embryotoxicity/teratogenicity studies in rats and rabbits, observed no effect dose levels were well below those for proposed clinical use (0.3 mg/kg/day for both the rat and rabbit; approximately 0.06 times the recommended human 24-hour dose of ribavirin). No maternal toxicity or effects on offspring were observed in a peri/postnatal toxicity study in rats dosed orally at up to 1 mg/kg/day (estimated human equivalent dose of 0.17 mg/kg based on body surface area adjustment for a 60 kg adult; approximately 0.01 times the maximum recommended human 24-hour dose of ribavirin).

Potential Risk to the Fetus

Ribavirin is known to accumulate in intracellular components from where it is cleared very slowly. It is not known whether ribavirin contained in sperm will exert a potential teratogenic effect upon fertilization of the ova. In a study in rats, it was concluded that dominant lethality was not induced by ribavirin at doses up to 200 mg/kg for 5 days (estimated human equivalent doses of 7.14 to 28.6 mg/kg, based on body surface area adjustment for a 60 kg adult; up to 1.7 times the maximum recommended human dose of ribavirin). However, because of the potential human teratogenic effects of ribavirin, male patients should be advised to take every precaution to avoid risk of pregnancy for their female partners.

Females of childbearing potential should not receive combination ribavirin capsules/INTRON A therapy unless they are using effective contraception (two reliable forms) during the therapy period. In addition, effective contraception should be utilized for 6 months posttherapy based on a multiple dose half-life (t1/2) of ribavirin of 12 days.

Male patients and their female partners must practice effective contraception (two reliable forms) during treatment with combination ribavirin capsules/INTRON A therapy and for the 6-month posttherapy period (e.g., 15 half-lives for ribavirin clearance from the body).

If pregnancy occurs in a patient or partner of a patient during treatment or during the 6 months after treatment cessation, physicians are encouraged to report such cases by calling the Ribavirin Pregnancy Registry at (800) 593-2214.

Ribavirin Pregnancy Registry

A Ribavirin Pregnancy Registry has been established to monitor maternal-fetal outcomes of pregnancies in female patients and female partners of male patients exposed to ribavirin during treatment and for six months following cessation of treatment. Physicians and patients are encouraged to report such cases by calling the Ribavirin Pregnancy Registry at 1-800-593-2214.

Nursing Mothers

It is not known whether ribavirin capsules and INTRON A are excreted in human milk. However, studies in mice have shown that mouse interferons are excreted into the milk. Because of the potential for serious adverse reactions from the drugs in nursing infants, a decision should be made whether to discontinue nursing or to discontinue combination ribavirin capsules/INTRON A therapy, taking into account the importance of the therapy to the mother.

Pediatric Use

Suicidal ideation or attempts occurred more frequently among pediatric patients compared to adult patients (2.4% versus 1%) during treatment and off therapy follow-up (see WARNINGS). As in adult patients, pediatric patients experienced other psychiatric adverse events (e.g., depression, emotional lability, somnolence), anemia, and neutropenia (see WARNINGS). During a 48 week course of therapy there was a decrease in the rate of linear growth (mean percentile assignment decrease of 7%) and a decrease in the rate of weight gain (mean percentile assignment decrease of 9%). A general reversal of these trends was noted during the 24 week post treatment period.

Injection site disorders, fever, anorexia, vomiting, and emotional lability occurred more frequently in pediatric patients compared to adult patients. Conversely, pediatric patients experienced less fatigue, dyspepsia, arthralgia, insomnia, irritability, impaired concentration, dyspnea, and pruritis compared to adult patients.

Geriatric Use

Clinical studies of combination therapy of ribavirin capsules taken together with INTRON A did not include sufficient numbers of subjects aged 65 and over to determine if they respond differently from younger subjects. In clinical trials, elderly subjects had a higher frequency of anemia (67%) than did younger patients (28%) (see WARNINGS).

In general, ribavirin capsules should be administered to elderly patients cautiously, starting at the lower end of the dosing range, reflecting the greater frequency of decreased renal, hepatic and/or cardiac function, and of concomitant disease or other drug therapy.

Ribavirin capsules are known to be substantially excreted by the kidney, and the risk of adverse reactions to ribavirin may be greater in patients with impaired renal function. Because elderly patients often have decreased renal function, care should be taken in dose selection. Renal function should be monitored and dosage adjustments of ribavirin should be made accordingly (see DOSAGE AND ADMINISTRATION: Guidelines for Dose Modification). Ribavirin capsules should not be used in elderly patients with creatinine clearance <50 mL/min (see WARNINGS).

Ribavirin capsules taken together with INTRON A should be used very cautiously in elderly patients with a history of psychiatric disorders (see WARNINGS).

ADVERSE REACTIONS

The safety of combination ribavirin capsules/INTRON A therapy was evaluated in controlled trials of 1010 HCV-infected adults who were previously untreated with interferon therapy and were subsequently treated for 24 or 48 weeks with combination ribavirin capsules/INTRON A therapy and in 173 HCV-infected patients who had relapsed after interferon therapy and were subsequently treated for 24 weeks with combination ribavirin capsules/INTRON A therapy. (See Description of Clinical Studies.) Overall, 19% and 6% of previously untreated and relapse patients, respectively, discontinued therapy due to adverse events in the combination arms compared to 13% and 3% in the interferon arms.

The primary toxicity of ribavirin is hemolytic anemia. Reductions in hemoglobin levels occurred within the first 1 to 2 weeks of therapy (see WARNINGS). Cardiac and pulmonary events associated with anemia occurred in approximately 10% of patients treated with ribavirin capsules/INTRON A therapy. (See WARNINGS.)

The most common psychiatric events occurring in US studies of previously untreated and relapse patients treated with ribavirin capsules/INTRON A therapy, respectively, were insomnia (39%, 26%), depression (34%, 23%), and irritability (27%, 25%). Suicidal behavior (ideation, attempts, and suicides) occurred in 1% of patients. (See WARNINGS.) In addition, the following spontaneous adverse events have been reported during the marketing surveillance of ribavirin capsules/INTRON A therapy: hearing disorder and vertigo. Very rarely, combination ribavirin capsules/INTRON A therapy may be associated with aplastic anemia.

Selected treatment-emergent adverse events that occurred in the US studies with ≥5% incidence are provided in TABLE 4 by treatment group. In general, the selected treatment-emergent adverse events reported with lower incidence in the international studies as compared to the US studies with the exception of asthenia, influenza-like symptoms, nervousness, and pruritus.

TABLE 4. Selected Treatment-Emergent Adverse Events: Previously Untreated and Relapse Patients
 | Percentage of Patients
 | US Previously Untreated Study |  |  |  | US Relapse Study
 | 24 weeks of treatment |  | 48 weeks of treatment |  | 24 weeks of treatment
Patients Reporting; Adverse Events [Patients reporting one or more adverse events. A patient may have reported more than one adverse event within a body system/organ class category.] | INTRON A; plus; Ribavirin; capsules; (N=228) | INTRON A; plus; Placebo; (N=231) | INTRON A; plus; Ribavirin; capsules; (N=228) | INTRON A; plus; Placebo; (N=225) | INTRON A; plus; Ribavirin; capsules; (N=77) | INTRON A; plus; Placebo; (N=76)
Application Site Disorders
Injection site inflammation | 13 | 10 | 12 | 14 | 6 | 8
Injection site reaction | 7 | 9 | 8 | 9 | 5 | 3
Body as a Whole –; General Disorders
Headache | 63 | 63 | 66 | 67 | 66 | 68
Fatigue | 68 | 62 | 70 | 72 | 60 | 53
Rigors | 40 | 32 | 42 | 39 | 43 | 37
Fever | 37 | 35 | 41 | 40 | 32 | 36
Influenza-like symptoms | 14 | 18 | 18 | 20 | 13 | 13
Asthenia | 9 | 4 | 9 | 9 | 10 | 4
Chest pain | 5 | 4 | 9 | 8 | 6 | 7
Central & Peripheral; Nervous System Disorders
Dizziness | 17 | 15 | 23 | 19 | 26 | 21
Gastrointestinal System Disorders
Nausea | 38 | 35 | 46 | 33 | 47 | 33
Anorexia | 27 | 16 | 25 | 19 | 21 | 14
Dyspepsia | 14 | 6 | 16 | 9 | 16 | 9
Vomiting | 11 | 10 | 9 | 13 | 12 | 8

TABLE 4. Selected Treatment-Emergent Adverse Events: Previously Untreated and Relapse Patients (continued)
 | Percentage of Patients
 | US Previously Untreated Study |  |  |  | US Relapse Study
 | 24 weeks of treatment |  | 48 weeks of treatment |  | 24 weeks of treatment
Patients Reporting; Adverse Events [Patients reporting one or more adverse events. A patient may have reported more than one adverse event within a body system/organ class category.] | INTRON A; plus; Ribavirin; capsules; (N=228) | INTRON A; plus; Placebo; (N=231) | INTRON A; plus; Ribavirin; capsules; (N=228) | INTRON A; plus; Placebo; (N=225) | INTRON A; plus; Ribavirin; capsules; (N=77) | INTRON A; plus; Placebo; (N=76)
Musculoskeletal System Disorders
Myalgia | 61 | 57 | 64 | 63 | 61 | 58
Arthralgia | 30 | 27 | 33 | 36 | 29 | 29
Musculoskeletal pain | 20 | 26 | 28 | 32 | 22 | 28
Psychiatric Disorders
Insomnia | 39 | 27 | 39 | 30 | 26 | 25
Irritability | 23 | 19 | 32 | 27 | 25 | 20
Depression | 32 | 25 | 36 | 37 | 23 | 14
Emotional lability | 7 | 6 | 11 | 8 | 12 | 8
Concentration impaired | 11 | 14 | 14 | 14 | 10 | 12
Nervousness | 4 | 2 | 4 | 4 | 5 | 4
Respiratory System Disorders
Dyspnea | 19 | 9 | 18 | 10 | 17 | 12
Sinusitis | 9 | 7 | 10 | 14 | 12 | 7
Skin and Appendages Disorders
Alopecia | 28 | 27 | 32 | 28 | 27 | 26
Rash | 20 | 9 | 28 | 8 | 21 | 5
Pruritus | 21 | 9 | 19 | 8 | 13 | 4
Special Senses, Other Disorders
Taste perversion | 7 | 4 | 8 | 4 | 6 | 5

Laboratory Values

Changes in selected hematologic values (hemoglobin, white blood cells, neutrophils, and platelets) during combination ribavirin capsules/INTRON A treatment are described below (see TABLE 5).

Hemoglobin

Hemoglobin decreases among patients on combination therapy began at Week 1, with stabilization by Week 4. In previously untreated patients treated for 48 weeks the mean maximum decrease from baseline was 3.1 g/dL in the US study and 2.9 g/dL in the International study. In relapse patients the mean maximum decrease from baseline was 2.8 g/dL in the US study and 2.6 g/dL in the International study. Hemoglobin values returned to pretreatment levels within 4 to 8 weeks of cessation of therapy in most patients.

Neutrophils

There were decreases in neutrophil counts in both the combination ribavirin capsules/INTRON A and INTRON A plus placebo dose groups. In previously untreated patients treated for 48 weeks the mean maximum decrease in neutrophil count in the US study was 1.3x 10^9/L and in the International study was 1.5 x 10^9/L. In relapse patients the mean maximum decrease in neutrophil count in the US study was 1.3 x 10^9/L and in the International study was 1.6 x 10^9/L. Neutrophil counts returned to pretreatment levels within 4 weeks of cessation of therapy in most patients.

Platelets

In both previously untreated and relapse patients mean platelet counts generally remained in the normal range in all treatment groups, however, mean platelet counts were 10% to 15% lower in the INTRON A plus placebo group than the ribavirin capsules/INTRON A group. Mean platelet counts returned to baseline levels within 4 weeks after treatment discontinuation.

Thyroid Function

Of patients who entered the previously untreated (24 and 48 week treatment) and relapse (24 week treatment) studies without thyroid abnormalities, approximately 3% to 6% and 1% to 2%, respectively, developed thyroid abnormalities requiring clinical intervention.

Bilirubin and Uric Acid

Increases in both bilirubin and uric acid, associated with hemolysis, were noted in clinical trials. Most were moderate biochemical changes and were reversed within 4 weeks after treatment discontinuation. This observation occurs most frequently in patients with a previous diagnosis of Gilbert’s syndrome. This has not been associated with hepatic dysfunction or clinical morbidity.

TABLE 5. Selected Hematologic Values During Treatment with Ribavirin Capsules plus INTRON A: Previously Untreated and Relapse Patients
 | Percentage of Patients
 | US Previously Untreated Study |  |  |  | US Relapse Study
 | 24 weeks of treatment |  | 48 weeks of treatment |  | 24 weeks of treatment
 | INTRON A; plus Ribavirin (N=228) | INTRON A; plus Placebo (N=231) | INTRON A; plus Ribavirin (N=228) | INTRON A; plus Placebo (N=225) | INTRON A; plus Ribavirin (N=77) | INTRON A; plus Placebo (N=76)
Hemoglobin (g/dL)
9.5-10.9 | 24 | 1 | 32 | 1 | 21 | 3
8.0-9.4 | 5 | 0 | 4 | 0 | 4 | 0
6.5-7.9 | 0 | 0 | 0 | 0.4 | 0 | 0
<6.5 | 0 | 0 | 0 | 0 | 0 | 0
Leukocytes (x10^9/L)
2.0-2.9 | 40 | 20 | 38 | 23 | 45 | 26
1.5-1.9 | 4 | 1 | 9 | 2 | 5 | 3
1.0-1.4 | 0.9 | 0 | 2 | 0 | 0 | 0
<1.0 | 0 | 0 | 0 | 0 | 0 | 0
Neutrophils (x10^9/L)
1.0-1.49 | 30 | 32 | 31 | 44 | 42 | 34
0.75-0.99 | 14 | 15 | 14 | 11 | 16 | 18
0.5-0.74 | 9 | 9 | 14 | 7 | 8 | 4
<0.5 | 11 | 8 | 11 | 5 | 5 | 8
Platelets (x10^9/L)
70-99 | 9 | 11 | 11 | 14 | 6 | 12
50-69 | 2 | 3 | 2 | 3 | 0 | 5
30-49 | 0 | 0.4 | 0 | 0.4 | 0 | 0
<30 | 0.9 | 0 | 1 | 0.9 | 0 | 0
Total Bilirubin (mg/dL)
1.5-3.0 | 27 | 13 | 32 | 13 | 21 | 7
3.1-6.0 | 0.9 | 0.4 | 2 | 0 | 3 | 0
6.1-12.0 | 0 | 0 | 0.4 | 0 | 0 | 0
>12.0 | 0 | 0 | 0 | 0 | 0 | 0

OVERDOSAGE

There is limited experience with overdosage. Acute ingestion of up to 20 grams of ribavirin capsules, INTRON A ingestion of up to 120 million units, and subcutaneous doses of INTRON A up to 10 times the recommended doses have been reported. Primary effects that have been observed are increased incidence and severity of the adverse events related to the therapeutic use of INTRON A and ribavirin capsules. However, hepatic enzyme abnormalities, renal failure, hemorrhage, and myocardial infarction have been reported with administration of single subcutaneous doses of INTRON A that exceed dosing recommendations.

There is no specific antidote for INTRON A or ribavirin capsules, and hemodialysis and peritoneal dialysis are not effective for treatment of overdose of either agent.

DOSAGE AND ADMINISTRATION

INTRON A Injection should be administered subcutaneously and ribavirin capsules should be administered orally. Ribavirin capsules may be administered without regard to food, but should be administered in a consistent manner. (See CLINICAL PHARMACOLOGY.)

Adults

The recommended dose of ribavirin capsules in patients 18 years of age and older depends on the patient’s body weight. The recommended doses of ribavirin capsules and INTRON A for adults are given in TABLE 6.

The recommended duration of treatment for patients previously untreated with interferon is 24 to 48 weeks. The duration of treatment should be individualized to the patient depending on baseline disease characteristics, response to therapy, and tolerability of the regimen (see Description of Clinical Studies and ADVERSE REACTIONS). After 24 weeks of treatment virologic response should be assessed. Treatment discontinuation should be considered in any patient who has not achieved an HCV-RNA below the limit of detection of the assay by 24 weeks. There are no safety and efficacy data on treatment for longer than 48 weeks in the previously untreated patient population.

In patients who relapse following interferon therapy, the recommended duration of treatment is 24 weeks. There are no safety and efficacy data on treatment for longer than 24 weeks in the relapse patient population.

TABLE 6. Recommended Adult Dosing
Body Weight | Ribavirin Capsules | INTRON A Injection
≤75 kg | 2 x 200 mg capsules AM,; 3 x 200 mg capsules PM; daily p.o. | 3 million; IU 3 times weekly s.c.
>75 kg | 3 x 200 mg capsules AM,; 3 x 200 mg capsules PM; daily p.o. | 3 million; IU 3 times weekly s.c.

Under no circumstances should ribavirin capsules be opened, crushed or broken (see CONTRAINDICATIONS and WARNINGS).

Dose Modifications

(See TABLE 7.)

In clinical trials, approximately 26% of patients required modification of their dose of ribavirin capsules, INTRON A Injection, or both agents. If severe adverse reactions or laboratory abnormalities develop during combination ribavirin capsules/INTRON A therapy the dose should be modified, or discontinued if appropriate, until the adverse reactions abate. If intolerance persists after dose adjustment, ribavirin capsules/INTRON A therapy should be discontinued.

Ribavirin capsules/INTRON A therapy should be administered with caution to patients with preexisting cardiac disease. Patients should be assessed before commencement of therapy and should be appropriately monitored during therapy. If there is any deterioration of cardiovascular status, therapy should be stopped. (See WARNINGS.)

For patients with a history of stable cardiovascular disease, a permanent dose reduction is required if the hemoglobin decreases by ≥2 g/dL during any 4-week period. In addition, for these cardiac history patients, if the hemoglobin remains <12 g/dL after 4 weeks on a reduced dose, the patient should discontinue combination ribavirin capsules/INTRON A therapy.

It is recommended that a patient whose hemoglobin level falls below 10 g/dL have his/her ribavirin capsules dose reduced to 600 mg daily (1 x 200 mg capsule AM, 2 x 200 mg capsules PM). A patient whose hemoglobin level falls below 8.5 g/dL should be permanently discontinued from ribavirin capsules/INTRON A therapy. (See WARNINGS.)

It is recommended that a patient who experiences moderate depression (persistent low mood, loss of interest, poor self image, and/or hopelessness) have his/her INTRON A dose temporarily reduced and/or be considered for medical therapy. A patient experiencing severe depression or suicidal ideation/attempt should be discontinued from ribavirin capsules/INTRON A therapy and followed closely with appropriate medical management. (See WARNINGS.)

TABLE 7. Guidelines for Dose Modifications
 | Dose Reduction [Study medication to be dose reduced is shown in parenthesis.]; Ribavirin capsules –; Adults 600 mg daily; INTRON A – Adults; 1.5 million IU TIW | Permanent; Discontinuation; of Treatment; Ribavirin capsules; and INTRON A
Hemoglobin | <10 g/dL; (Ribavirin capsules) | <8.5 g/dL
Cardiac History; Patients Only | ≥2 g/dL decrease; during any 4-week; period during treatment; (Ribavirin capsules/; INTRON A) | <12 g/dL after; 4 weeks of dose; reduction
White blood count | <1.5 x 10^9/L (INTRON A) | <1.0 X 10^9/L
Neutrophil count | <0.75 x 10^9/L (INTRON A) | <0.5 X 10^9/L
Platelet count | Adults: <50 x 10^9/L; (INTRON A) | Adults: <25 x 10^9/L

Administration of INTRON A Injection

At the discretion of the physician, the patient may self-administer the INTRON A. [See illustrated Appendix to Medication Guide on ribavirin capsules for instructions.]

The Intron A Injection is supplied as a clear and colorless solution. The appropriate INTRON A dose should be withdrawn from the vial or set on the multidose pen and injected subcutaneously. The INTRON A Injection supplied with the B-D Safety Lok™ syringes contain a plastic sleeve to be pulled over the needle after use. The syringe locks with an audible click when the green stripe on the safety sleeve covers the red stripe on the needle. After administration of INTRON A Injection, it is essential to follow the procedure for proper disposal of syringes and needles. [See Appendix to Medication Guide on ribavirin capsules for detailed instructions.]

Vial/Pen Label Strength | Fill Volume | Concentration
3 million IU vial | 0.5 mL | 3 million IU/0.5 mL
18 million IU multidose vial [This is a multidose vial which contains a total of 22.8 million IU of interferon alfa-2b, recombinant per 3.8 mL in order to provide the delivery of six 0.5-mL doses, each containing 3 million IU of interferon alfa-2b, recombinant (for a label strength of 18 million IU).] | 3.8 mL | 3 million IU/0.5 mL
18 million IU multidose pen [This is a multidose pen which contains a total of 22.5 million IU of interferon alfa-2b, recombinant per 1.5 mL in order to provide the delivery of six 0.2-mL doses, each containing 3 million IU of interferon alfa-2b, recombinant (for a label strength of 18 million IU).] | 1.5 mL | 3 million IU/0.2 mL

Parenteral drug products should be inspected visually for particulate matter and discoloration prior to administration, whenever solution and container permit. INTRON A Injection may be administered using either sterilized glass or plastic disposable syringes.

Stability

INTRON A Injection provided in vials is stable at 35°C (95°F) for up to 7 days and at 30°C (86°F) for up to 14 days. INTRON A Injection provided in a multidose pen is stable at 30°C (86°F) for up to 2 days. The solution is clear and colorless.

HOW SUPPLIED

Ribavirin capsules, 200 mg are white, opaque, hard gelatin capsules imprinted (in blue) RIBAVIRIN over 200 mg on cap and GG 608 on body.

They are supplied by State of Florida DOH Central Pharmacy as follows:

NDC | Strength | Quantity/Form | Color | Source Prod. Code
53808-0781-1 | 200 mg | 30 Capsules in a Blister Pack | WHITE | 0781-2043

Dispense in a tight container as defined in the USP.

Store at 25°C (77°F); excursions permitted to 15°-30°C (59°-86°F) [see USP Controlled Room Temperature].

INTRON A Injection is a clear, colorless solution packaged in single dose and multidose vials, and a multidose pen.

INTRON A Injection and the INTRON A Multidose Pen should be stored refrigerated between 2° and 8°C (36° and 46°F).

INTRON® A is a registered trademark of Schering Corporation.

Mylanta® is a registered trademark of Johnson & Johnson-Merck Consumer Pharmaceuticals Co.

REBETOL® is a registered trademark of Schering Corporation.

REBETRON® is a registered trademark of Schering Corporation.

MEDICATION GUIDE

Ribavirin Capsules 200 mg

Read this medication guide carefully before you begin taking ribavirin capsules, and each time you refill your prescription in case new information has been included. This summary does not tell you everything about ribavirin capsules. Your health care provider is the best source of information about this medicine. After reading this medication guide, talk with your health care provider if you have any questions about ribavirin.

What is the most important information I should know about therapy with ribavirin capsules?

- Ribavirin capsules may cause birth defects or death of an unborn child. Therefore, if you are pregnant or your sexual partner is pregnant, do not take ribavirin. If you could become pregnant, you must not become pregnant during therapy and for 6 months after you have stopped therapy. During this time you must use 2 forms of birth control, and you must have pregnancy tests that show that you are not pregnant.
  Female sexual partners of male patients being treated with ribavirin must not become pregnant during treatment and for 6 months after treatment has stopped. Therefore, you must use 2 forms of birth control during this time.
  If you or a female sexual partner becomes pregnant, you should tell your health care provider. There is a Ribavirin Pregnancy Registry that collects information about pregnancy outcomes in female patients and female partners of male patients exposed to ribavirin. You or your health care provider are encouraged to contact the Ribavirin Pregnancy Registry at 1-800-593-2214.
  Be assured that any information you tell the Registry will be kept confidential. (See “What should I avoid while taking ribavirin capsules?”)

- Ribavirin capsules can cause a dangerous drop in your red blood cell count. Ribavirin capsules can cause anemia, which is a decrease in the number of red blood cells. This can be dangerous, especially if you have heart or breathing problems. Tell your health care provider before taking ribavirin if you have ever had any of these problems. Your health care provider should check your red blood cell count before you start therapy and often during the first 4 weeks of therapy. Your red blood cell count may be checked more often if you have any heart or breathing problems.
- Do not take ribavirin capsules alone to treat hepatitis C infection. Ribavirin capsules should be used in combination with interferon alfa-2b (INTRON®^1 A) for treating chronic hepatitis C infection in adults.

Please read the Appendix to this Medication Guide. It has additional important information about combination therapy not covered in this guide.

What is ribavirin?

Ribavirin is an antiviral drug. It is used in combination with interferon alfa-2b to treat some patients with chronic hepatitis C infection. It is not known how ribavirin and interferon alfa-2b work together to fight hepatitis C infection. (See the Appendix to this Medication Guide.)

It is not known if treatment with ribavirin and interferon alfa-2b will cure hepatitis C virus infections or prevent cirrhosis, liver failure, or liver cancer that can be caused by hepatitis C virus infections. It is not known if treatment with ribavirin and interferon alfa-2b will prevent an infected person from infecting another person with the hepatitis C virus.

Who should not take ribavirin capsules?

Do not use these medicines if:

- You are a female and you are pregnant or plan to become pregnant at any time during your treatment with ribavirin or during the 6 months after your treatment has ended.
- You are a male patient with a female sexual partner who is pregnant or plans to become pregnant at any time while you are being treated with ribavirin or during the 6 months after your treatment has ended. (See “What is the most important information I should know about therapy with ribavirin capsules?” and “What should I avoid while taking ribavirin capsules?”)
- You are breast-feeding. Ribavirin may pass through your milk and harm your baby. Talk with your provider about whether you should stop breast-feeding.
- You are allergic to any of the ingredients in ribavirin capsules. See the ingredients listed at the end of this Medication Guide on ribavirin capsules.

Tell your health care provider before starting treatment with ribavirin capsules in combination with interferon alfa-2b, if you have any of the following medical conditions:

- mental health problems, such as depression or anxiety. Ribavirin/Interferon alfa-2b therapy may make them worse. Tell your health care provider if you are being treated or had treatment in the past for any mental problems, including depression, suicidal behavior, or a feeling of loss of contact with reality, such as hearing voices or seeing things that are not there (psychosis). Tell your health care provider if you take any medicines for these problems.
- high blood pressure, heart problems, or have had a heart attack. Ribavirin capsules may worsen heart problems. Patients who have had certain heart problems should not take ribavirin capsules.
- blood disorders, including anemia (low red blood cell count), thalassemia (Mediterranean anemia), and sickle-cell anemia. Ribavirin capsules can reduce the number of red blood cells you have. This may make you feel dizzy or weak and could worsen any heart problems you might have.
- kidney problems. If your kidneys do not work properly, you may experience worse side effects from ribavirin therapy and require a lower dose.
- liver problems (other than hepatitis C infection).
- organ transplant, and are taking medicine that keeps your body from rejecting your transplant (suppresses your immune system).
- thyroid disease. Ribavirin/Interferon alfa-2b therapy may make your thyroid disease worse or harder to treat. Ribavirin/Interferon alfa-2b therapy may be stopped if you develop thyroid problems that cannot be controlled by medication.
- lung problems. Ribavirin/Interferon alfa-2b therapy can cause breathing problems or worsen breathing problems you already have.
- alcoholism or drug abuse or addiction
- cancer
- infection with hepatitis B virus and/or human immunodeficiency virus, the virus that causes AIDS.
- diabetes. Ribavirin/Interferon alfa-2b therapy may make your diabetes worse or harder to treat.
- past interferon treatment for hepatitis C virus infection that did not work for you.

For more information see the Appendix to this Medication Guide.

How should I take ribavirin capsules?

Your health care provider has determined the correct dose of ribavirin capsules based on your weight. Your health care provider may lower your dose of ribavirin if you have side effects.

- It is important to follow your dosing schedule and your health care provider’s instructions on how to take your medicines.
- If you take ribavirin capsules with INTRON A, you can take it with or without food. However, you should take it the same way every day.
- Take the medicine for as long as prescribed and do not take more than the recommended dose.
- If you miss a dose of ribavirin capsules, take the missed dose as soon as possible during the same day. If an entire day has gone by, check with your health care provider about what to do. Do not double the next dose.
- Tell your health care provider if you are taking or planning to take other prescription or non-prescription medicines, including vitamin and mineral supplements, and herbal medicines.
- Tell your provider before taking ribavirin capsules if you have ever had any heart or breathing problems. Your provider should check your red blood cell count before starting therapy and often during the first 4 weeks of therapy. Your red blood cell count may be checked more frequently if you have had heart or breathing problems.
- Females taking ribavirin capsules or female sexual partners of male patients taking ribavirin capsules must have a pregnancy test before treatment begins, every month during treatment, and for 6 months after treatment ends to make sure there is no pregnancy.

What should I avoid while taking ribavirin capsules?

Avoid the following during ribavirin capsule treatment:

- Pregnancy: If you or your sexual partner becomes pregnant during treatment with ribavirin capsules or in the 6 months after treatment ends, tell your health care provider right away. (See “What is the most important information I should know about therapy with ribavirin capsules?” at the beginning of this Medication Guide.)
  Talk with your health care provider about how to avoid pregnancy. If you or your sexual partner becomes pregnant while on ribavirin or during the 6 months after your treatment ends, you must report the pregnancy to your health care provider right away. Your health care provider should call the Ribavirin Pregnancy Registry at 1-800-593-2214. Your health care provider will be asked to give follow-up information about the pregnancy. Any information about your pregnancy that is reported about you will be confidential.
- Breastfeeding. The medicine may pass through your milk and harm the baby.
- Drinking alcohol, including beer, wine, and liquor. This may make your liver disease worse.
- Taking other medicines. Take only medicines prescribed or approved by your health care provider. These include prescription and non-prescription medicines and herbal supplements.

What are the most common side effects of ribavirin capsules?

The most serious possible side effects of ribavirin capsules are:

- Harm to unborn children. Ribavirin capsules may cause birth defects or death of an unborn child. (For more details, see “What is the most important information I should know about therapy with ribavirin capsules?”)
- Anemia. Anemia is a reduction in the number of red blood cells you have, which can be dangerous, especially if you have heart or breathing problems. Tell your health care provider right away if you feel tired, have chest pain or shortness of breath. These may be signs of low red blood cell counts.

Tell your provider right away if you have any of the following symptoms. They may be signs of a serious side effect:

- trouble breathing
- hives or swelling
- chest pain
- severe stomach or lower back pain
- bloody diarrhea or bloody stools (bowel movements). These may appear black and tarry.
- bruising
- other bleeding

The most common side effects of ribavirin capsules are:

- feeling tired
- nausea and appetite loss
- rash and itching
- cough

This summary does not include all possible side effects of ribavirin therapy Talk to your health care provider, if you do not feel well while taking ribavirin capsules. Your health care provider can give you more information about managing your side effects.

What should I know about the hepatitis C infection?

Hepatitis C infection is a disease caused by a virus that infects the liver. This liver infection becomes a continuing (chronic) condition in most patients. Patients with chronic hepatitis C infection may develop cirrhosis, liver cancer, and liver failure. The virus is spread from one person to another by contact with the infected person’s blood. You should talk to your health care provider about ways to prevent you from infecting others.

How do I store my ribavirin capsules?

Store ribavirin capsules at 25°C (77°F) ; excursions permitted to 15°-30°C (59°-86°F) [see USP Controlled Room Temperature].

General advice about prescription medicines

Do not use ribavirin capsules for conditions for which they were not prescribed. If you have any concern about ribavirin capsules, ask your health care provider. Your health care provider or pharmacist can give you information about ribavirin capsules that was written for health care professionals. Do not give this medicine to other people, even if they have the same condition you have.

Ingredients: Ribavirin capsules contain ribavirin and the inactive ingredients croscarmellose sodium, hypromellose, magnesium stearate, mannitol, and povidone. The capsule shell consists of gelatin and titanium dioxide. The capsule is printed with edible blue pharmaceutical ink which is made of FD&C Blue #2 aluminum lake, propylene glycol, shellac and titanium dioxide.

THIS MEDICATION GUIDE HAS BEEN APPROVED BY THE U.S. FOOD AND DRUG ADMINISTRATION.

APPENDIX to Medication Guide on Ribavirin Capsules

[Note: In addition to REBETOL®^2 (ribavirin) Capsules, Schering Corporation also markets REBETRON®^3. REBETRON is a copackaged combination therapy containing REBETOL (ribavirin, USP) and INTRON A (interferon alfa-2b, recombinant) Injection. REBETRON has medication guides that provide information on the combination use of REBETOL (ribavirin, USP) and INTRON A. This Appendix provides medication guide information on ribavirin capsules taken together with INTRON A that corresponds to information in the medication guides for REBETRON.]

Read this Appendix carefully before you begin taking ribavirin capsules together with INTRON A, and each time you refill your prescription in case there is new information. This summary does not tell you everything about ribavirin capsules taken together with INTRON A. Your health care provider is the best source of information about these medicines. After reading this Appendix, talk with your health care provider if you have any questions about this treatment.

What is the most important information I should know about ribavirin capsules taken together with INTRON A?

- Ribavirin capsules taken together with INTRON A may cause birth defects and/or death of an unborn child. Therefore, if you are pregnant, you must not take therapy of ribavirin capsules taken together with INTRON A. If you could become pregnant, you must not become pregnant during therapy and for six months after you have stopped therapy. During this time you must use two forms of birth control, and you must have pregnancy tests that show that you are not pregnant.
  Female sexual partners of male patients being treated with ribavirin capsules must not become pregnant during treatment and for six months after treatment has stopped. Therefore, two forms of birth control must be used during this time.
  If you or a female sexual partner becomes pregnant, you should tell your health care provider. There is a Ribavirin Pregnancy Registry that collects information about pregnancy outcomes in female patients and female partners of male patients exposed to ribavirin. You or your health care provider are encouraged to contact the Ribavirin Pregnancy Registry at 1-800-593-2214.
- Treatment with ribavirin capsules and INTRON A products can cause a dangerous drop in your blood cell counts.
  Ribavirin capsules taken together with INTRON A can cause anemia, which is a decrease in the number of red blood cells. This can be dangerous, especially if you have heart or breathing problems. Tell your health care provider before taking ribavirin capsules together with INTRON A if you have ever had any of these problems. Your health care provider should check your red blood cell count before starting therapy and often during the first 4 weeks of therapy. Your red blood cell count may be checked more often if you have heart or breathing problems.
- Ribavirin capsules taken together with INTRON A can cause a dangerous drop in the number of cells that help fight infections and stop bleeding, which might cause you to have an infection or abnormal bleeding.
- Serious mental problems: Ribavirin capsules taken together with INTRON A may cause or worsen mood or behavioral problems.
  These can include irritability (getting easily upset) and depression (feeling low, feeling bad about yourself). Some patients think about hurting or killing themselves or other people, and some have killed themselves (suicide) or hurt themselves or others. If you experience any of these thoughts or symptoms you should tell your healthcare provider right away. See “What are the possible side effects of ribavirin capsules taken together with INTRON A?” for important information on signs of mental problems.
- You should not take ribavirin capsules alone to treat your hepatitis C virus infection. Ribavirin capsules should be used only in combination with interferon alfa-2b (INTRON A) for the treatment of chronic hepatitis C infection.

What is therapy of ribavirin capsules taken together with INTRON A?

Ribavirin capsules taken together with INTRON A is a treatment for some people who have chronic hepatitis C infection. It consists of two separate medicines, ribavirin capsules and INTRON A Injection (interferon), used in combination. INTRON A helps the body’s immune system fight infections. The antiviral drug ribavirin is made by Sandoz Inc. It is not known how ribavirin capsules and INTRON A work together to fight hepatitis C infection. Ribavirin capsules should not be used alone to treat chronic hepatitis C infection.

It is not known if treatment with ribavirin capsules taken together with INTRON A will cure hepatitis C virus infections or prevent cirrhosis, liver failure, or liver cancer that can be caused by hepatitis C virus infections. It is not known if treatment with ribavirin capsules taken together with INTRON A will prevent you from infecting another person with the hepatitis C virus.

You should use therapy of ribavirin capsules taken together with INTRON A only if you have never been treated or your hepatitis C has returned after interferon therapy.

Who should not take ribavirin capsules together with INTRON A?

Do not use these medicines if:

- You are a female and you are pregnant or plan to become pregnant at any time during your treatment with ribavirin capsules taken together with INTRON A or during the 6 months after your treatment has ended.
- You are a male patient with a female sexual partner who is pregnant or plans to become pregnant at any time while you are being treated during treatment with ribavirin capsules taken together with INTRON A or during the 6 months after your treatment has ended. Please see “What is the most important information I should know about ribavirin capsules taken together with INTRON A?” at the beginning of this Appendix.
- You are breastfeeding. Ribavirin capsules and INTRON A products may pass through your milk and harm your baby. Talk with your health care provider about whether you should stop breast-feeding.
- You have autoimmune hepatitis (hepatitis caused by cells in your body attacking each other) because treatment with ribavirin capsules and INTRON A can make this kind of liver problem worse.
- You are allergic to any of the ingredients in ribavirin capsules or INTRON A Injection, or to any alpha interferon. (See ingredients listed at the end of this Appendix.)

Tell your health care provider before starting therapy of ribavirin capsules taken together with INTRON A if you have any of the following medical conditions or other serious medical problems:

- mental health problems, such as depression or anxiety. Ribavirin capsules taken together with INTRON A may make them worse. Tell your health care provider if you are being treated for a mental illness or had treatment in the past for any mental problems, including depression, suicidal behavior, or psychosis. Psychosis is loss of contact with reality, such as hearing voices or seeing things that are not there.
- high blood pressure, other heart problems, or have had a heart attack. The medicines in the therapy of ribavirin capsules taken together with INTRON A may worsen heart problems. Patients who have had certain heart problems should not take the therapy of ribavirin capsules together with INTRON A.
- blood disorders, including anemia (low red blood cell count), thalassemia (Mediterranean anemia), and sickle-cell anemia. Ribavirin capsules taken together with INTRON A can reduce the number of red blood cells you have. This may make you feel dizzy or weak and could worsen any heart problems you might have.
- kidney problems. If your kidneys do not work well, you may get worse side effects from ribavirin capsules taken together with INTRON A and need a dose adjustment.
- liver problems (other than hepatitis C infection)
- organ transplant, and are taking medicine that keeps your body from rejecting your transplant (suppresses your immune system)
- thyroid disease. Ribavirin capsules taken together with INTRON A may make your thyroid disease worse or harder to treat. Ribavirin capsules taken together with INTRON A may be stopped if you develop thyroid abnormalities that cannot be controlled by medication.
- lung problems. Ribavirin/Interferon alfa-2b therapy can cause breathing problems or worsen breathing problems you already have.
- alcoholism or drug abuse or addiction
- cancer
- infection with hepatitis B virus or human immunodeficiency virus (HIV), the virus that causes AIDS.
- diabetes. Ribavirin capsules taken together with INTRON A may make your diabetes worse or harder to treat.
- past interferon treatment for hepatitis C virus infection that did not work for you.

How should I take ribavirin capsules together with INTRON A?

- Your health care provider has determined the correct doses of ribavirin capsules and INTRON A. Your doses of ribavirin capsules and INTRON A may be lowered if you have side effects.
- Under no circumstance should ribavirin capsules be opened, crushed, or broken.

The recommended doses of INTRON A Injection and ribavirin capsules for patients 18 years of age and older are shown in the table below.

If your weight is: | Take this many; ribavirin capsules; each day: | Inject this amount; of INTRON A under; your skin; (subcutaneously)
165 pounds; or less | 2 capsules in; the AM; 3 capsules in; the PM | 3 million; international units; 3 times a week
More than; 165 pounds | 3 capsules in; the AM; 3 capsules in; the PM | 3 million; international units; 3 times a week

- You can take your ribavirin capsules with or without food, but you should take it the same way every day.
- It is important to follow your dosing schedule and your health care provider’s instructions on how to take your medicines.
- Take the medicines for as long as they are prescribed, and do not take more than the recommended doses.
- If you miss a dose of ribavirin capsules, take the missed dose as soon as possible during the same day. If an entire day has gone by, check with your health care provider about what to do. Do not double the next dose.
- If you miss a dose of INTRON A, take the missed dose as soon as possible during the same day or on the next day, and continue your regular dosing schedule. If several days go by without taking INTRON A, check with your health care provider about what to do. Do not double the next dose.
- Tell your health care provider if you are taking or planning to take other prescription or non-prescription medicines, including vitamin and mineral supplements and herbal medicines.

Instructions on how to inject INTRON A are at the end of this Appendix.

What should I avoid while taking ribavirin capsules together with INTRON A?

- Pregnancy: If you or your sexual partner becomes pregnant, tell your health care provider right away. (See “What is the most important information I should know about therapy with ribavirin capsules taken together with INTRON A?” at the beginning of this Appendix.) Talk with your health care provider about how to avoid pregnancy.

If you or your sexual partner becomes pregnant while being treated with ribavirin capsules taken together with INTRON A or during the 6 months after treatment ends, you must report the pregnancy to your health care provider right away. Your health care provider should call the Ribavirin Pregnancy Registry toll-free at 1-800-593-2214. Your health care provider will be asked to give follow-up information about the pregnancy. Any information about your pregnancy that is reported about you will be confidential.

- Breastfeeding. The medicine may pass through your milk and harm the baby.
- Drinking alcohol, including beer, wine and liquor because this may make your liver disease worse.
- Do not inject yourself with INTRON A if it is discolored or contains particles.
- Taking any medicines other than those prescribed or approved by your health care provider
- Ask your health care provider if there are other things you should avoid, in addition to alcohol (beer, wine, liquor), prescription and nonprescription drugs, and alternative medications (herbal medicine).

What are the possible side effects of ribavirin capsules taken together with INTRON A?

Harm to unborn children. Ribavirin capsules taken together with INTRON A can harm your unborn child. It can cause birth defects and may kill your unborn child. (For more details, see “What is the most important information I should know about ribavirin capsules taken together with INTRON A?” at the beginning of this Appendix.)

- Anemia. Ribavirin capsules taken together with INTRON A causes anemia (a reduction in the number of red blood cells you have) which can be dangerous, especially if you have heart, or breathing problems. Tell your health care provider right away if you feel tired, have chest pain or shortness of breath. These may be signs of low red blood counts.
- Infections. INTRON A therapy may lower your white blood cell count, making it easier for you to get serious infections. You must have your blood tested regularly during treatment to check for this problem.
- Mental Problems. Tell your health care provider if you have ever had any mental illness, including depression, suicidal behavior, or psychosis (loss of contact with reality such as hearing voices or seeing things that are not there). Also, tell your health care provider if you are taking any medications for these problems. Tell your health care provider right away if you have the following:
- Start to feel unusually sad or have crying spells
- Lose interest in your usual activities
- Have changes in your normal sleep patterns
- Become more irritable than usual
- Lose your appetite
- Become unusually tired
- Have trouble concentrating
- Withdraw from family and friends
- Have thoughts about hurting yourself or others.

Tell your health care provider right away if you have any of the following symptoms. They may be signs of a serious side effect:

- trouble breathing, hives or swelling
- chest pain
- severe stomach or lower back pain
- bloody diarrhea or bloody stools (bowel movements). These may appear to be black and tarry.
- high fever
- bruising
- bleeding
- decreased vision

What are the most common side effects of ribavirin capsules taken together with INTRON A?

- “Flu-like” symptoms. These include headache, feeling very tired (fatigue), muscle aches, and fever. These get better as treatment continues. You can reduce some of these flu-like symptoms by injecting your INTRON A about 2 hours before bedtime. Some health care providers suggest taking non-prescription pain and fever reducers, such as acetaminophen or ibuprofen before taking INTRON A. This may be helpful to prevent or relieve the fever and headache.
- Feeling tired
- Hair thinning
- Rash and itching
- Nausea and appetite loss
- Abdominal pain with nausea and vomiting
- Trouble breathing
- Trouble with your vision
- Trouble sleeping at night

This summary does not include all possible side effects of combination therapy. You should talk to your health care provider, if you do not feel well while taking ribavirin capsules and INTRON A. Your health care provider can give you more information about managing your side effects.

What should I know about the hepatitis C virus?

Hepatitis C infection is a disease caused by a virus that infects the liver. This liver infection becomes a continuing (chronic) condition in most patients. Patients with chronic hepatitis C infection may develop cirrhosis, liver cancer, and liver failure. The virus is spread from one person to another by contact with the infected person’s blood. You should talk to your health care provider about ways to prevent you from infecting others.

How do I Inject INTRON A?

- When you have been trained to do it properly. If you have any questions, contact your health care provider before injecting INTRON A.
- Use the sterile technique taught by your health care provider. Use disposable needles after each use, and throw them away properly as directed by your health care provider, nurse, or pharmacist.
- If someone else gives you your injection, that person should be trained in the use of sterile technique and how to avoid an accidental needle stick.

Preparing the INTRON A Dose

IMPORTANT: Before each use, the liquid in the vial (small bottle) should be clear, colorless to light yellow, and without particles. Do not use the medicine if you see particles or the color is not correct. Call your doctor, nurse, or pharmacist to find out what to do if this happens.

1. Check the date printed on the INTRON A carton to make sure that the expiration date has not passed.
2. Wash your hands well and remove the protective plastic cap from the top of the INTRON A vial.
3. Remove the protective plastic wrapper from the syringe provided (Figure A). The safety sleeve should be tight against the flange for use and moved over the needle only when ready for disposal, as instructed in step 6.
  Figure A
4. Clean the rubber stopper on the top of the INTRON A vial with an alcohol swab.
5. Remove the protective cap from the syringe needle. Ensure safety sleeve is pushed firmly against the syringe flange so that the needle is fully exposed. Fill the syringe with air by pulling the plunger to the level that represents your correct dose (Figure B).
  Figure B
6. Hold the INTRON A vial upright without touching the cleaned top of the vial with your hands (Figure C).
  Figure C
7. Insert the needle into the vial containing the INTRON A solution and inject the air into the vial (Figure D).
  Figure D
8. Turn vial and syringe upside down in one hand. Be sure tip of needle is in the INTRON A solution. Your other hand will be free to move the plunger. Pull back on plunger slowly to draw the correct dose into syringe (Figure E).
  Figure E
9. Remove the needle from the vial (Figure F) and check for air bubbles in the syringe. If you see any bubbles, tap the syringe gently. Then, with the needle pointing up, push the plunger slowly until the bubbles disappear.
  Figure F
10. Replace the needle cap. If the solution is cold, warm the syringe between your hands. Lay the syringe down on a flat surface so that needle does not touch anything.

Subcutaneous (under the skin) Injection

1. Select the site for injection
  • The best sites for injection are tissues with a layer of fat between skin and muscle, such as the
  • thigh
  • outer surface of the upper arm
  • abdomen (stomach area), except the navel (belly button) or waistline
  • If you are very thin, use only the thigh or outer surface of the arm for injection.
  • Do not inject INTRON A solution in the same place repeatedly. Change your injection site in a regular pattern.
  Use an alcohol swab to cleanse the skin where the injection is to be made. Wait for area to dry.
2. Remove the cap from the needle. Ensure the safety sleeve is pushed firmly against the syringe flange so that the needle is fully exposed. Hold the syringe with one hand, as you would hold a pencil. With the other hand, pinch approximately a 2-inch fold of loose skin.
3. With a quick dart-like motion, push the needle about 1/4 inch into the pinched skin at an angle of 45° to 90°.
  After the needle is in, remove hand used to pinch skin and use it to hold syringe barrel. Pull back the plunger very slightly with one hand. If blood comes into the syringe, the needle has entered a blood vessel. Do not inject. Withdraw and discard needle and syringe as instructed in step 6 below. Prepare a new syringe and inject at a new site. (Follow steps 2 and 3.)
4. If blood does not appear in the syringe, gently push the plunger all the way down.
5. Hold an alcohol swab near the needle and pull the needle straight out of the skin. Press the alcohol swab over the injection site for several seconds. Do not massage (rub) the injection site. If there is bleeding, cover the area with an adhesive bandage.
6. After use, firmly grasp the safety sleeve and pull over the exposed needle until you hear a click, and the green stripe on the safety sleeve covers the red stripe on the needle.
7. Use disposable syringe only once to ensure sterility of syringe and needle. Dispose of syringe and needle as directed.
  Your health care professional should tell you about the proper handling and disposal of all syringes and needles and the importance of not reusing any syringes or needles.
  Your health care professional should give you a container for throwing away used needles and syringes. Throw away the full container according to directions provided by your doctor.
8. After 2 hours, check injection site for signs of inflammation, such as redness, swelling, or tenderness. If there are signs of inflammation, contact your doctor.

HOW TO USE YOUR INTRON A Multidose Pen

When you are ready to give your injection prepare your pen as follows (NOTE: Boldface print indicates ACTION STEPS):

1. First check that you have the correct INTRON A multidose pen as prescribed by your health care provider, (i.e. the six doses of 3 MIU INTRON A multidose pen which have a brown push button and a brown color coding strip).
2. Pull off the cap of the pen and disinfect the rubber membrane (see Diagram C) with one alcohol wipe.
  Diagram C
3. Remove the protective tab from the Novofine^4 needle. Note that the rear portion of the needle is revealed once the protective tab is removed (see Diagram D).
  Diagram D
4. Gently push the Novofine^4 needle onto the pen as shown in Diagram E. (Notice that the rear portion of the needle described in Step 3 will pierce through the rubber membrane that you disinfected previously.) Now screw the needle onto the INTRON A multidose pen securely by turning it in a clockwise direction (see Diagram F).
  Diagram E
  Diagram F
5. First, pull off the outer needle cap (Diagram G). Then, pull off the inner needle cap carefully, bearing in mind that the needle will now be exposed (Diagram H). Keep the outer needle cap for later use.
  The pen is now ready to use. Since a small amount of air may collect in the needle and reservoir during storage, the next step is to remove any air bubbles.
  Diagram G
  Diagram H
6. Hold the INTRON A multidose pen with the needle point upwards.
7. Tap the reservoir with your finger so that any air bubbles rise to the top of the reservoir, just below the needle (Diagram I).
  Diagram I
8. Hold the pen by the barrel and turn the reservoir in the direction as indicated by the arrow in Diagram J (clockwise) until you feel it click.
  Diagram J
9. Keeping the pen pointing upwards, press the push button up fully and see if a drop of INTRON A solution appears at the needle tip (notice the drop at the tip of needle in Diagram K).
  Diagram K
10. If no drop appears then repeat Steps 7, 8, and 9 until a drop appears at the needle tip. Note: Some air may still remain in the pen, but this is not important as you have removed the air from the needle and the dose will be accurate.
11. Replace the INTRON A multidose pen cap with the ‘triangle’ opposite the dosage indicator as seen in Diagram L.
  The pen is now ready to set the dose. For the next step hold the pen in the middle of the barrel. This will allow the push button to move freely, ensuring that the correct dose is set.
  Diagram L
12. To set the required dose, hold the pen horizontally by the barrel with one hand. With the other hand, turn the cap in a clockwise direction indicated by the arrow in Diagram M. You will observe the push button rising, indicating the dose set. To set a 3 MIU dose, turn the cap 2 full turns (10 clicks) = 3.0 MIU.
  Note: If your health care provider has prescribed a dose other than 3 MIU, the correct dose can be set by turning the cap as many times as indicated as follows:
  1 full turn (5 clicks) = 1.5 MIU
  3 full turns (15 clicks) = 4.5 MIU
  4 full turns (20 clicks) = 6.0 MIU
  The push button scale will show you the dose set (see Diagram N). At that point check that you have the correct dose.
  Diagram M
  Diagram N
13. After each complete turn make sure that the triangle is opposite the dosage indicator (see Diagram O). If you have set a wrong dose, simply turn the cap back (counter-clockwise) as far as you can until the push button is fully home and start again. Once the correct dose is set, you are ready to give the injection.
  Diagram O
14. To give the injection, remove the pen cap from the needle. With one hand, pinch a 2-inch fold of loose skin.
15. With your other hand, pick up the pen and hold it as you would a pencil. Insert the needle into the pinched skin at an angle of approximately 45° (see Diagram P) then press the push button down fully.
  If blood comes into the pen, do not inject. Withdraw the needle and consult your physician or pharmacist.
  Diagram P
16. Leave the needle in place for a few seconds, while holding down the push button, to allow the INTRON A Solution to distribute under the skin.
17. Slowly release the push button, then remove the needle.
18. Carefully replace the outerneedle cap using a scooping motion (See Diagram Q).
  Diagram Q
19. Completely unscrew the needle assembly using a counterclockwise turning motion as show in Diagram R. Then carefully lift it off the pen and discard the capped needle (see Diagram S).
  Diagram R
  Diagram S
20. Replace the pen cap with the triangle once again opposite the dosage indicator as shown in Diagram T.
  Diagram T

Instructional leaflet and video are available through your healthcare provider.

How do I store my medications?

STORAGE OF RIBAVIRIN CAPSULES

Store ribavirin capsules at 25°C (77°F); excursions permitted to 15°-30°C (59°-86°F) [see USP Controlled Room Temperature].

STORAGE OF INTRON A INJECTION VIAL AND MULTIDOSE PEN

INTRON A Injection vial and multidose pen should be stored in the refrigerator between 36° and 46°F (2° and 8°C), not in the freezer.

General advice about prescription medicines

Do not use ribavirin capsules or INTRON A for conditions for which they were not prescribed. If you have any concern about therapy of taking ribavirin capsules together with INTRON A, ask your health care provider. Your health care provider or pharmacist can give you information about ribavirin capules taken together with INTRON A that was written for health care professionals. Do not give these medicines to other people, even if they have the same condition you have.

Ingredients: Ribavirin capsules contain ribavirin and the inactive ingredients croscarmellose sodium, hypromellose, magnesium stearate, mannitol, and povidone. The capsule shell consists of gelatin and titanium dioxide. The capsule is printed with edible blue pharmaceutical ink which is made of FD&C Blue #2 aluminum lake, propylene glycol, shellac and titanium dioxide.

THIS MEDICATION GUIDE HAS BEEN APPROVED BY THE U.S. FOOD AND DRUG ADMINISTRATION.

1. INTRON® A is a registered trademark of Schering Corporation.
2. REBETOL® is a registered trademark of Schering Corporation.
3. REBETRON® is a registered trademark of Schering Corporation.
4. Novofine is a registered trademark of Novo Nordisk.

Sandoz Inc.

Princeton, NJ 08540

This Product was Repackaged By:

State of Florida DOH Central Pharmacy
104-2 Hamilton Park Drive
Tallahassee, FL 32304
United States